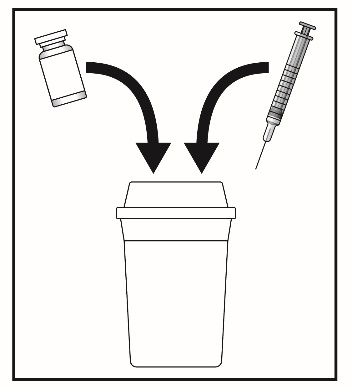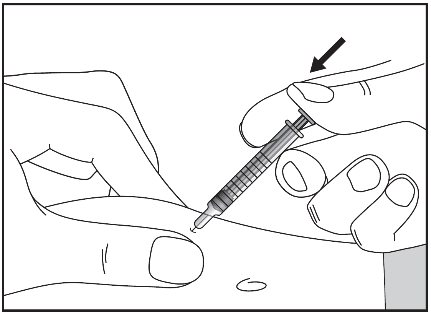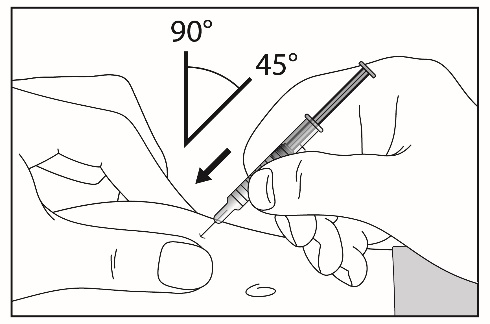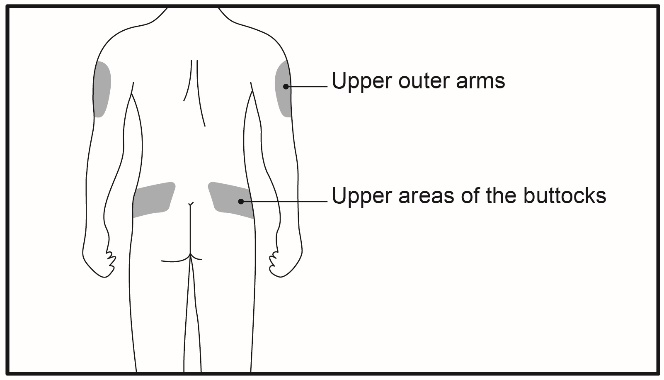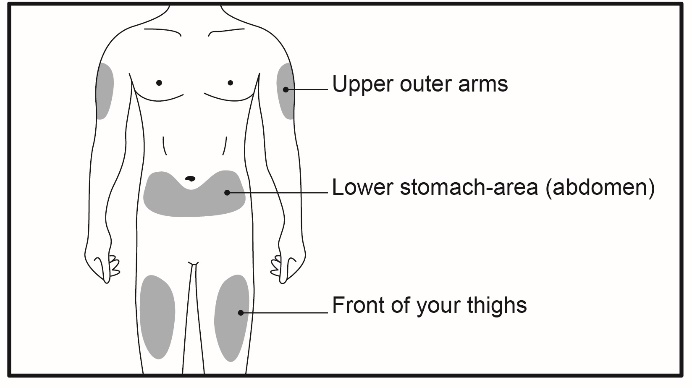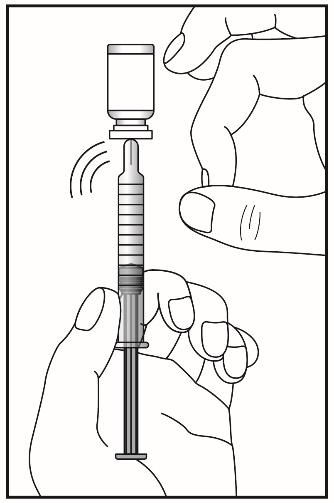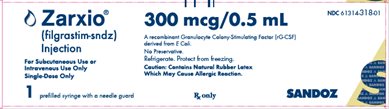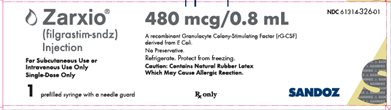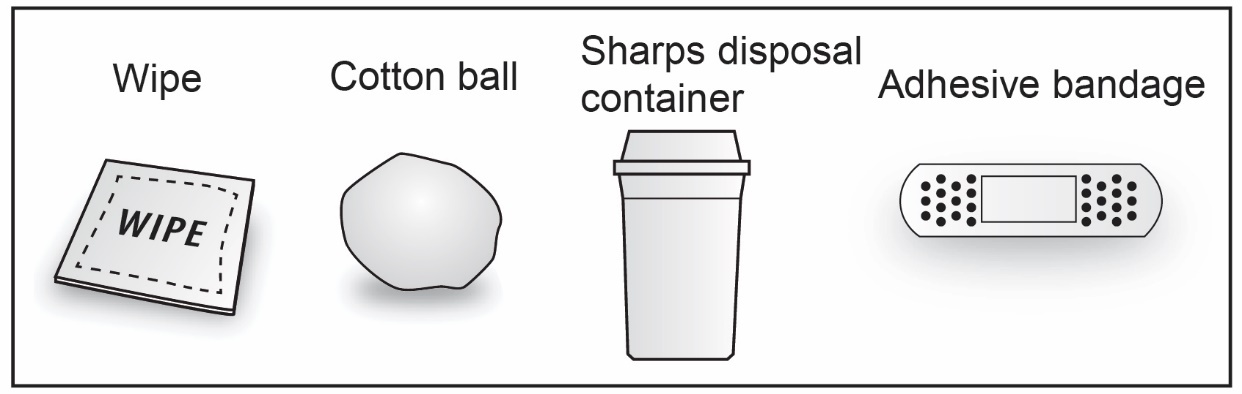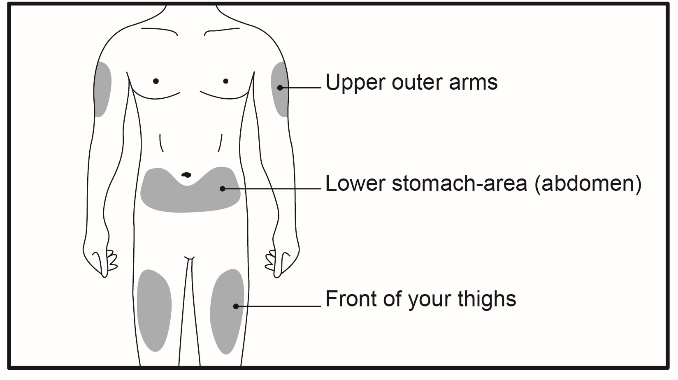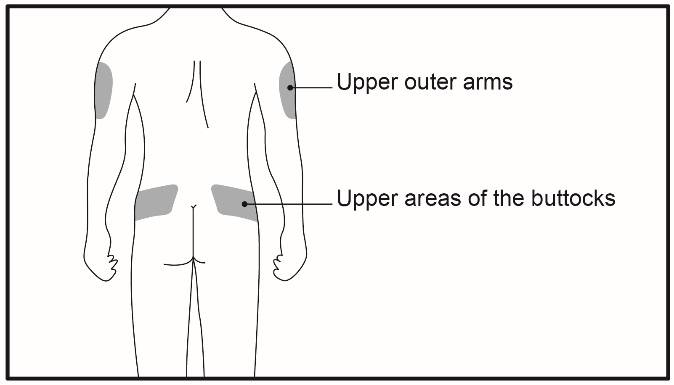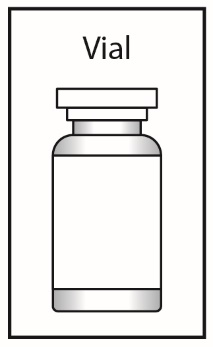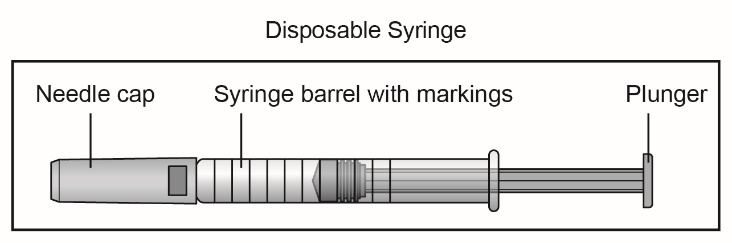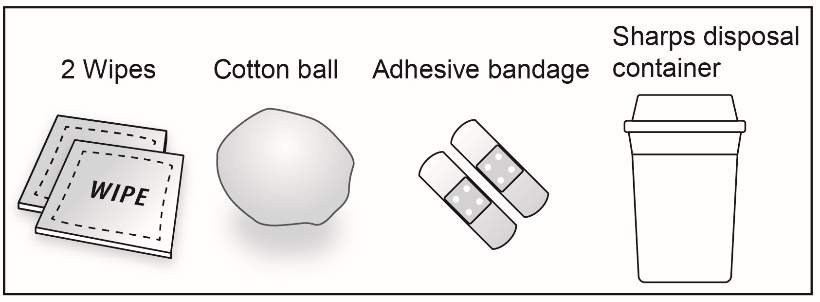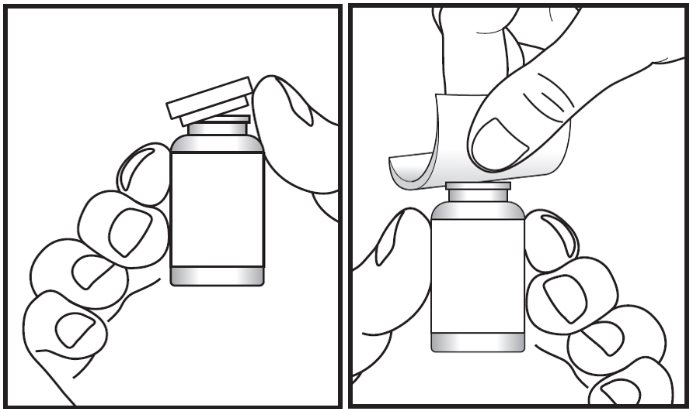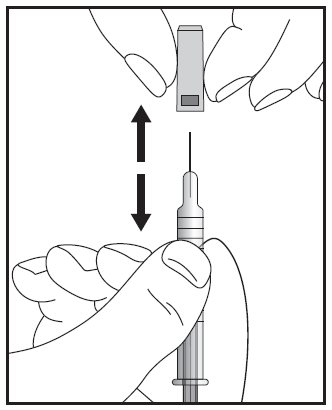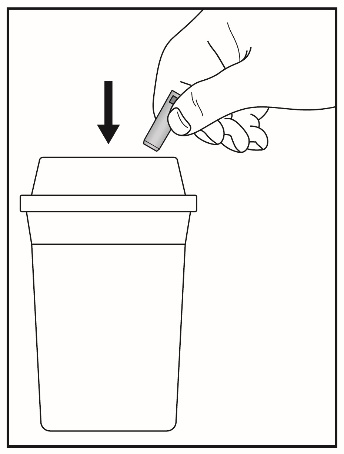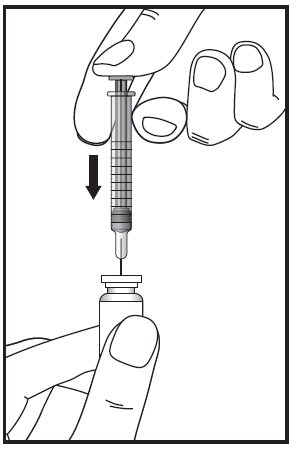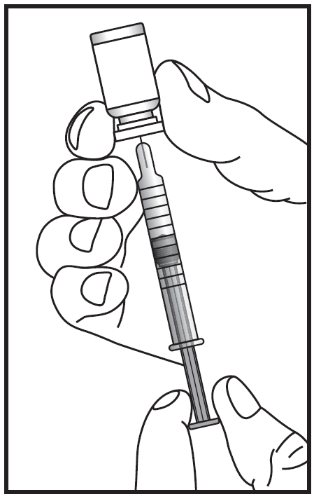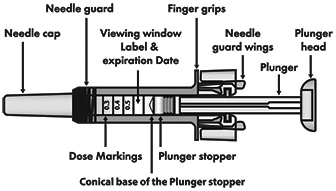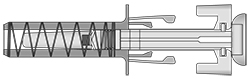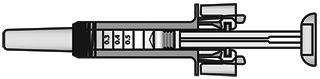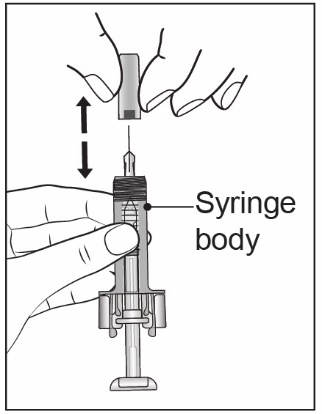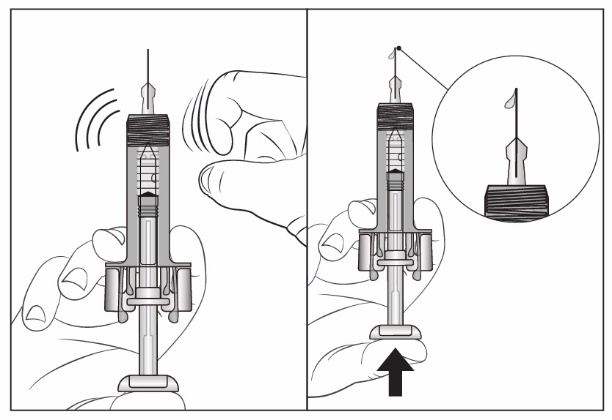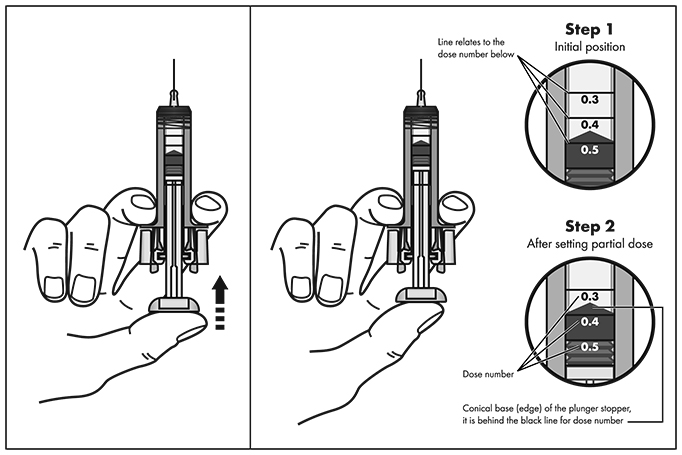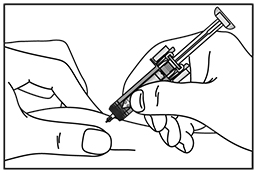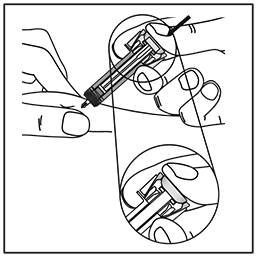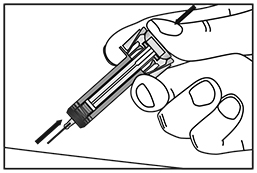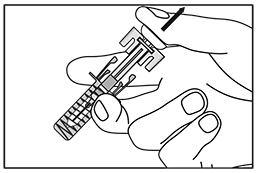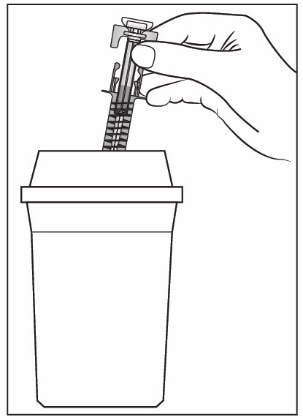 DRUG LABEL: ZARXIO
NDC: 61314-318 | Form: INJECTION, SOLUTION
Manufacturer: Sandoz Inc.
Category: prescription | Type: HUMAN PRESCRIPTION DRUG LABEL
Date: 20250829

ACTIVE INGREDIENTS: FILGRASTIM 300 ug/0.5 mL
INACTIVE INGREDIENTS: GLUTAMIC ACID 0.736 mg/0.5 mL; SORBITOL 25 mg/0.5 mL; POLYSORBATE 80 0.02 mg/0.5 mL; SODIUM HYDROXIDE; WATER

HIGHLIGHTS OF PRESCRIBING INFORMATION

These highlights do not include all the information needed to use ZARXIO safely and effectively. See full prescribing information for ZARXIO.
ZARXIO® (filgrastim-sndz) injection, for subcutaneous or intravenous use
Initial U.S. Approval: 2015
ZARXIO (filgrastim-sndz) is biosimilar* to NEUPOGEN (filgrastim).

RECENT MAJOR CHANGES

Indications and Usage: Patients Acutely Exposed to Myelosuppressive Doses of Radiation (Hematopoietic Syndrome of Acute Radiation Syndrome) (1.6) | 10/2024
Dosage and Administration: Dosage in Patients Acutely Exposed to Myelosuppressive Doses of Radiation (Hematopoietic Syndrome of Acute Radiation Syndrome) (2.5) | 10/2024
Dosage and Administration: Important Administration Instructions (2.6) | 08/2024

1 INDICATIONS AND USAGE

ZARXIO is a leukocyte growth factor indicated to

- Decrease the incidence of infection‚ as manifested by febrile neutropenia‚ in patients with nonmyeloid malignancies receiving myelosuppressive anti‑cancer drugs associated with a significant incidence of severe neutropenia with fever (1.1)
- Reduce the time to neutrophil recovery and the duration of fever, following induction or consolidation chemotherapy treatment of patients with acute myeloid leukemia (AML) (1.2)
- Reduce the duration of neutropenia and neutropenia-related clinical sequelae‚ e.g.‚ febrile neutropenia, in patients with nonmyeloid malignancies undergoing myeloablative chemotherapy followed by bone marrow transplantation (BMT) (1.3)
- Mobilize autologous hematopoietic progenitor cells into the peripheral blood for collection by leukapheresis (1.4)
- Reduce the incidence and duration of sequelae of severe neutropenia (e.g.‚ fever‚ infections‚ oropharyngeal ulcers) in symptomatic patients with congenital neutropenia‚ cyclic neutropenia‚ or idiopathic neutropenia (1.5)
- Increase survival in patients acutely exposed to myelosuppressive doses of radiation (Hematopoietic Syndrome of Acute Radiation Syndrome) (1.6)

2 DOSAGE AND ADMINISTRATION

- Patients with cancer receiving myelosuppressive chemotherapy or induction and/or consolidation chemotherapy for AML
  - Recommended starting dose is 5 mcg/kg/day subcutaneous injection, short intravenous infusion (15 to 30 minutes), or continuous intravenous infusion. See Full Prescribing Information for recommended dosage adjustments and timing of administration (2.1)
- Patients with cancer undergoing bone marrow transplantation
  - 10 mcg/kg/day given as an intravenous infusion no longer than 24 hours. See Full Prescribing Information for recommended dosage adjustments and timing of administration. (2.2)
- Patients undergoing autologous peripheral blood progenitor cell collection and therapy
  - 10 mcg/kg/day subcutaneous injection (2.3)
  - Administer for at least 4 days before first leukapheresis procedure and continue until last leukapheresis (2.3)
- Patients with congenital neutropenia
  - Recommended starting dose is 6 mcg/kg subcutaneous injection twice daily (2.4)
- Patients with cyclic or idiopathic neutropenia
  - Recommended starting dose is 5 mcg/kg subcutaneous injection daily (2.4)
- Patients acutely exposed to myelosuppressive doses of radiation
  - 10 mcg/kg/day subcutaneous injection (2.5)
- Direct administration of less than 0.3 mL (180 mcg) using ZARXIO prefilled syringe is not recommended due to potential for dosing errors (2.6)

3 DOSAGE FORMS AND STRENGTHS

Vial

- Injection: 300 mcg/mL in a single-dose-vial (3)
- Injection: 480 mcg/1.6 mL (300 mcg/mL) in a single-dose-vial (3)

Prefilled Syringe

- Injection: 300 mcg/0.5 mL in a single-dose prefilled syringe with BD UltraSafe Passive® Needle Guard (3)
- Injection: 480 mcg/0.8 mL in a single-dose prefilled syringe with BD UltraSafe Passive® Needle Guard (3)

4 CONTRAINDICATIONS

Patients with a history of serious allergic reactions to human granulocyte colony-stimulating factors such as filgrastim products or pegfilgrastim products. (4)

5 WARNINGS AND PRECAUTIONS

- Fatal splenic rupture: Evaluate patients who report left upper abdominal or shoulder pain for an enlarged spleen or splenic rupture. (5.1)
- Acute respiratory distress syndrome (ARDS): Evaluate patients who develop fever and lung infiltrates or respiratory distress for ARDS. Discontinue ZARXIO in patients with ARDS. (5.2)
- Serious allergic reactions, including anaphylaxis: Permanently discontinue ZARXIO in patients with serious allergic reactions. (5.3)
- Fatal sickle cell crises: Discontinue ZARXIO if sickle cell crisis occurs. (5.4)
- Glomerulonephritis: Evaluate and consider dose-reduction or interruption of ZARXIO if causality is likely. (5.5)
- Myelodysplastic Syndrome (MDS) and Acute Myeloid Leukemia (AML): Monitor patients with breast and lung cancer using ZARXIO in conjunction with chemotherapy and/or radiotherapy for signs and symptoms of MDS/AML. (5.8)
- Thrombocytopenia: Monitor platelet counts. (5.9)
- Aortitis: Aortitis has been reported in patients receiving filgrastim products. Discontinue ZARXIO if aortitis is suspected. (5.15)

6 ADVERSE REACTIONS

Most common adverse reactions in patients:

- With nonmyeloid malignancies receiving myelosuppressive anti-cancer drugs (≥ 5% difference in incidence compared to placebo) are pyrexia, pain, rash, cough, and dyspnea. (6.1)
- With AML (≥ 2% difference in incidence) are pain, epistaxis and rash. (6.1)
- With nonmyeloid malignancies undergoing myeloablative chemotherapy followed by BMT (≥ 5% difference in incidence) is rash. (6.1)
- Undergoing peripheral blood progenitor cell mobilization and collection (≥ 5% incidence) are bone pain, pyrexia and headache. (6.1)
- With severe chronic neutropenia (SCN) (≥ 5% difference in incidence) are pain, anemia, epistaxis, diarrhea, hypoesthesia and alopecia. (6.1)

*Biosimilar means that the biological product is approved based on data demonstrating that it is highly similar to an FDA-approved biological product, known as a reference product, and that there are no clinically meaningful differences between the biosimilar product and the reference product. Biosimilarity of ZARXIO has been demonstrated for the condition(s) of use (e.g., indication(s), dosing regimen(s)), strength(s), dosage form(s), and route(s) of administration described in its Full Prescribing Information.

To report SUSPECTED ADVERSE REACTIONS, contact Sandoz Inc. at 1-800-525-8747 or FDA at 1-800-FDA-1088 or www.fda.gov/medwatch.

FULL PRESCRIBING INFORMATION

1 INDICATIONS AND USAGE

1.1 Patients with Cancer Receiving Myelosuppressive Chemotherapy

ZARXIO is indicated to decrease the incidence of infection‚ as manifested by febrile neutropenia‚ in patients with nonmyeloid malignancies receiving myelosuppressive anti-cancer drugs associated with a significant incidence of severe neutropenia with fever [see Clinical Studies (14.1)].

1.2 Patients with Acute Myeloid Leukemia Receiving Induction or Consolidation Chemotherapy

ZARXIO is indicated for reducing the time to neutrophil recovery and the duration of fever, following induction or consolidation chemotherapy treatment of patients with acute myeloid leukemia (AML) [see Clinical Studies (14.2)].

1.3 Patients with Cancer Undergoing Bone Marrow Transplantation

ZARXIO is indicated to reduce the duration of neutropenia and neutropenia-related clinical sequelae‚ e.g.‚ febrile neutropenia, in patients with nonmyeloid malignancies undergoing myeloablative chemotherapy followed by bone marrow transplantation [see Clinical Studies (14.3)].

1.4 Patients Undergoing Autologous Peripheral Blood Progenitor Cell Collection and Therapy

ZARXIO is indicated for the mobilization of autologous hematopoietic progenitor cells into the peripheral blood for collection by leukapheresis [see Clinical Studies (14.4)].

1.5 Patients with Severe Chronic Neutropenia

ZARXIO is indicated for chronic administration to reduce the incidence and duration of sequelae of neutropenia (e.g.‚ fever‚ infections‚ oropharyngeal ulcers) in symptomatic patients with congenital neutropenia‚ cyclic neutropenia‚ or idiopathic neutropenia [see Clinical Studies (14.5)].

1.6 Patients Acutely Exposed to Myelosuppressive Doses of Radiation (Hematopoietic Syndrome of Acute Radiation Syndrome)

ZARXIO is indicated to increase survival in patients acutely exposed to myelosuppressive doses of radiation [see Clinical Studies (14.6)].

2 DOSAGE AND ADMINISTRATION

2.1 Dosage in Patients with Cancer Receiving Myelosuppressive Chemotherapy or Induction and/or Consolidation Chemotherapy for AML

The recommended starting dosage of ZARXIO is 5 mcg/kg/day‚ administered as a single daily injection by subcutaneous injection‚ by short intravenous infusion (15 to 30 minutes)‚ or by continuous intravenous infusion. Obtain a complete blood count (CBC) and platelet count before instituting ZARXIO therapy and monitor twice weekly during therapy. Consider dose escalation in increments of 5 mcg/kg for each chemotherapy cycle‚ according to the duration and severity of the absolute neutrophil count (ANC) nadir. Recommend stopping ZARXIO if the ANC increases beyond 10‚000/mm^3 [see Warnings and Precautions (5.10)].

Administer ZARXIO at least 24 hours after cytotoxic chemotherapy. Do not administer ZARXIO within the 24-hour period prior to chemotherapy [see Warnings and Precautions (5.13)]. A transient increase in neutrophil count is typically seen 1 to 2 days after initiation of ZARXIO therapy. Therefore, to ensure a sustained therapeutic response‚ administer ZARXIO daily for up to 2 weeks or until the ANC has reached 10‚000/mm^3 following the expected chemotherapy-induced neutrophil nadir. The duration of ZARXIO therapy needed to attenuate chemotherapy-induced neutropenia may be dependent on the myelosuppressive potential of the chemotherapy regimen employed.

2.2 Dosage in Patients with Cancer Undergoing Bone Marrow Transplantation

The recommended dosage of ZARXIO following bone marrow transplantation (BMT) is 10 mcg/kg/day given as an intravenous infusion no longer than 24 hours. Administer the first dose of ZARXIO at least 24 hours after cytotoxic chemotherapy and at least 24 hours after bone marrow infusion. Monitor CBCs and platelet counts frequently following marrow transplantation.

During the period of neutrophil recovery‚ titrate the daily dosage of ZARXIO against the neutrophil response (see Table 1).

Table 1. Recommended Dosage Adjustments During Neutrophil Recovery in Patients with Cancer Following BMT

Absolute Neutrophil Count | ZARXIO Dosage Adjustment
When ANC greater than 1,000/mm^3 for 3 consecutive days | Reduce to 5 mcg/kg/day [If ANC decreases to less than 1,000/mm^3 at any time during the 5 mcg/kg/day administration‚ increase ZARXIO to 10 mcg/kg/day‚ and then follow the above steps.]
Then, if ANC remains greater than 1,000/mm^3 for 3 more consecutive days | Discontinue ZARXIO
Then, if ANC decreases to less than 1,000/mm^3 | Resume at 5 mcg/kg/day

2.3 Dosage in Patients Undergoing Autologous Peripheral Blood Progenitor Cell Collection and Therapy

The recommended dosage of ZARXIO for the mobilization of autologous peripheral blood progenitor cells (PBPC) is 10 mcg/kg/day given by subcutaneous injection. Administer ZARXIO for at least 4 days before the first leukapheresis procedure and continue until the last leukapheresis. Although the optimal duration of ZARXIO administration and leukapheresis schedule have not been established‚ administration of filgrastim for 6 to 7 days with leukaphereses on days 5‚ 6‚ and 7 was found to be safe and effective [see Clinical Studies (14.4)]. Monitor neutrophil counts after 4 days of ZARXIO‚ and discontinue ZARXIO if the white blood cell (WBC) count rises to greater than 100‚000/mm^3.

2.4 Dosage in Patients with Severe Chronic Neutropenia

Prior to starting ZARXIO in patients with suspected chronic neutropenia, confirm the diagnosis of severe chronic neutropenia (SCN) by evaluating serial CBCs with differential and platelet counts‚ and evaluating bone marrow morphology and karyotype. The use of ZARXIO prior to confirmation of a correct diagnosis of SCN may impair diagnostic efforts and may thus impair or delay evaluation and treatment of an underlying condition‚ other than SCN‚ causing the neutropenia.

The recommended starting dosage in patients with Congenital Neutropenia is 6 mcg/kg as a twice daily subcutaneous injection and the recommended starting dosage in patients with Idiopathic or Cyclic Neutropenia is 5 mcg/kg as a single daily subcutaneous injection.

Dosage Adjustments in Patients with Severe Chronic Neutropenia

Chronic daily administration is required to maintain clinical benefit. Individualize the dosage based on the patient’s clinical course as well as ANC. In the SCN postmarketing surveillance study, the reported median daily doses of filgrastim were: 6 mcg/kg (congenital neutropenia), 2.1 mcg/kg (cyclic neutropenia), and 1.2 mcg/kg (idiopathic neutropenia). In rare instances, patients with congenital neutropenia have required doses of filgrastim greater than or equal to 100 mcg/kg/day.

Monitor CBCs for Dosage Adjustments

During the initial 4 weeks of ZARXIO therapy and during the 2 weeks following any dosage adjustment‚ monitor CBCs with differential and platelet counts. Once a patient is clinically stable‚ monitor CBCs with differential and platelet counts monthly during the first year of treatment. Thereafter, if the patient is clinically stable, less frequent routine monitoring is recommended.

2.5 Dosage in Patients Acutely Exposed to Myelosuppressive Doses of Radiation (Hematopoietic Syndrome of Acute Radiation Syndrome)

The recommended dosage of ZARXIO is 10 mcg/kg as a single daily subcutaneous injection for patients exposed to myelosuppressive doses of radiation. Administer ZARXIO as soon as possible after suspected or confirmed exposure to radiation doses greater than 2 gray (Gy).

Estimate a patient’s absorbed radiation dose (i.e., level of radiation exposure) based on information from public health authorities, biodosimetry if available, or clinical findings such as time to onset of vomiting or lymphocyte depletion kinetics.

Obtain a baseline CBC and then serial CBCs approximately every third day until the ANC remains greater than 1,000/mm^3 for 3 consecutive CBCs. Do not delay administration of ZARXIO if a CBC is not readily available.

Continue administration of ZARXIO until the ANC remains greater than 1,000/mm^3 for 3 consecutive CBCs or exceeds 10,000/mm^3 after a radiation-induced nadir.

2.6 Important Administration Instructions

ZARXIO (for subcutaneous use or intravenous use) is supplied in single-dose vials and in single-dose prefilled syringes [see Dosage Forms and Strengths (3)].

Administration Instructions for Subcutaneous Injection

Inject ZARXIO subcutaneously in the outer area of upper arms, abdomen, thighs, or upper outer areas of the buttock. If patients or caregivers are to administer ZARXIO, instruct them in appropriate injection technique and ask them to follow the subcutaneous injection procedures in the Instructions for Use for prefilled syringe with BD UltraSafe Passive ® Needle Guard or for the vial.

If the patient or caregiver misses a dose of ZARXIO, instruct them to contact their healthcare provider.

Patients who will self-administer and caregivers who will administer to the patient may benefit from training by a healthcare professional. Training should aim to demonstrate to those patients and caregivers how to measure the dose of ZARXIO, and the focus should be on ensuring that a patient or caregiver can successfully perform all of the steps in the Instructions for Use for the vial or prefilled syringe with BD UltraSafe Passive® Needle Guard. If a patient or caregiver is not able to demonstrate that they can measure the dose and administer the product successfully, you should consider whether the patient is an appropriate candidate for self-administration of ZARXIO prefilled syringe or whether the patient would benefit from the ZARXIO vial presentation. If a patient or caregiver experiences difficulty measuring the required dose, especially if it is other than the entire content of the ZARXIO prefilled syringe, use of the ZARXIO vial may be considered [see Instructions for Use].

Instructions for the Prefilled Syringe

ZARXIO prefilled syringe with BD UltraSafe Passive® Needle Guard is not designed to allow for direct administration of doses of less than 0.3 mL (180 mcg). The spring-mechanism of the needle guard apparatus affixed to the prefilled syringe interferes with the visibility of the graduation markings on the syringe barrel corresponding to 0.1 mL and 0.2 mL. The visibility of these markings is necessary to accurately measure doses of ZARXIO less than 0.3 mL (180 mcg) for direct administration to patients. Thus, the direct administration to patients requiring doses of less than 0.3 mL (180 mcg) is not recommended due to the potential for dosing errors. If less than 0.3 mL is needed the ZARXIO single-dose vial should be used.

Persons with latex allergies should not administer the ZARXIO prefilled syringe, because the needle cap contains natural rubber latex (derived from latex). For latex sensitive individuals the ZARXIO vial should be considered as the vial stopper is not made with natural rubber latex.

Prior to use‚ remove the prefilled syringe from the refrigerator and allow ZARXIO to reach room temperature [between 20°C to 25°C (68°F to 77°F)] for a minimum of 30 minutes. If not used immediately, the prefilled syringe may be stored at room temperature for up to 8 days. Discard any prefilled syringe left at room temperature for greater than 8 days. Parenteral drug products should be inspected visually for particulate matter and discoloration prior to administration, whenever solution and container permit (the solution is clear and colorless to slightly yellowish). Do not administer ZARXIO if particulates or discoloration are observed.

Discard unused portion of ZARXIO in prefilled syringes. Do not save unused drug for later administration.

Instructions for the Single-dose vial

Prior to use‚ remove the vial from the refrigerator and allow ZARXIO to reach room temperature for a minimum of 30 minutes. If not used immediately, the vial may be stored at room temperature for up to 8 days. Discard any vial left at room temperature for greater than 8 days. Parenteral drug products should be inspected visually for particulate matter and discoloration prior to administration, whenever solution and container permit (the solution is clear and colorless to slightly yellowish). Do not administer ZARXIO if particulates or discoloration are observed.

Discard the unused portion of ZARXIO in single-dose vial and do not re-enter the vial. Do not save unused drug for later administration.

Administration Instructions for Dilution

If required for intravenous administration, ZARXIO may be diluted in 5% Dextrose Injection, USP to concentrations between 5 mcg/mL and 15 mcg/mL. ZARXIO diluted to concentrations from 5 mcg/mL to 15 mcg/mL should be protected from adsorption to plastic materials by the addition of Albumin (Human) to a final concentration of 2 mg/mL. When diluted in 5% Dextrose Injection, USP or 5% Dextrose plus Albumin (Human)‚ ZARXIO is compatible with glass, polyvinylchloride, polyolefin, and polypropylene.

Do not dilute with Sodium Chloride Injection at any time because the product may precipitate.

Diluted ZARXIO solution from ZARXIO prefilled syringe can be stored at room temperature [between 20℃ to 25℃ (68℉ to 77℉)] for up to 24 hours. This 24‑hour time period includes the time during room temperature storage of the infusion solution and the duration of the infusion.

Diluted ZARXIO solution from ZARXIO vial can be stored refrigerated [2°C to 8°C (36°F to 46°F)] for up to 24 hours or at room temperature [between 20℃ to 25℃ (68℉ to 77℉)] for up to 4 hours, including the time during room temperature storage of the infusion solution and the duration of the infusion.

3 DOSAGE FORMS AND STRENGTHS

ZARXIO is a clear, colorless to slightly yellowish solution available as:

Vial:

- Injection: 300 mcg/mL in a single-dose vial
- Injection: 480 mcg/1.6 mL (300 mcg/mL) in a single-dose vial

Prefilled Syringe:

- Injection: 300 mcg/0.5 mL in a single-dose prefilled syringe
- Injection: 480 mcg/0.8 mL in a single-dose prefilled syringe

4 CONTRAINDICATIONS

ZARXIO is contraindicated in patients with a history of serious allergic reactions to human granulocyte colony-stimulating factors such as filgrastim products or pegfilgrastim products [see Warnings and Precautions (5.3)].

5 WARNINGS AND PRECAUTIONS

5.1 Splenic Rupture

Splenic rupture, including fatal cases, has been reported following the administration of filgrastim products. Evaluate patients who report left upper abdominal or shoulder pain for an enlarged spleen or splenic rupture.

5.2 Acute Respiratory Distress Syndrome

Acute respiratory distress syndrome (ARDS) has been reported in patients receiving filgrastim products. Evaluate patients who develop fever and lung infiltrates or respiratory distress for ARDS. Discontinue ZARXIO in patients with ARDS.

5.3 Serious Allergic Reactions

Serious allergic reactions, including anaphylaxis, have been reported in patients receiving filgrastim products. The majority of reported events occurred upon initial exposure. Provide symptomatic treatment for allergic reactions. Allergic reactions, including anaphylaxis, in patients receiving filgrastim products can recur within days after the discontinuation of initial anti-allergic treatment. Permanently discontinue ZARXIO in patients with serious allergic reactions. ZARXIO is contraindicated in patients with a history of serious allergic reactions to human granulocyte colony-stimulating factors such as filgrastim products or pegfilgrastim products.

5.4 Sickle Cell Disorders

Severe and sometimes fatal sickle cell crises can occur in patients with sickle cell disorders receiving filgrastim products. Discontinue ZARXIO if sickle cell crisis occurs.

5.5 Glomerulonephritis

Glomerulonephritis has occurred in patients receiving filgrastim products. The diagnoses were based upon azotemia, hematuria (microscopic and macroscopic), proteinuria, and renal biopsy. Generally, events of glomerulonephritis resolved after dose-reduction or discontinuation of filgrastim products. If glomerulonephritis is suspected, evaluate for cause. If causality is likely, consider dose-reduction or interruption of ZARXIO.

5.6 Alveolar Hemorrhage and Hemoptysis

Alveolar hemorrhage manifesting as pulmonary infiltrates and hemoptysis requiring hospitalization have been reported in healthy donors treated with filgrastim products undergoing peripheral blood progenitor cell (PBPC) collection mobilization. Hemoptysis resolved with discontinuation of filgrastim products. The use of ZARXIO for PBPC mobilization in healthy donors is not an approved indication.

5.7 Capillary Leak Syndrome

Capillary leak syndrome (CLS) has been reported after G-CSF administration, including filgrastim products, and is characterized by hypotension, hypoalbuminemia, edema and hemoconcentration. Episodes vary in frequency, severity and may be life-threatening if treatment is delayed. Patients who develop symptoms of capillary leak syndrome should be closely monitored and receive standard symptomatic treatment, which may include a need for intensive care.

5.8 Myelodysplastic Syndrome (MDS) and Acute Myeloid Leukemia (AML)

Patients with Severe Chronic Neutropenia

Confirm the diagnosis of SCN before initiating ZARXIO therapy.

MDS and AML have been reported to occur in the natural history of congenital neutropenia without cytokine therapy. Cytogenetic abnormalities, transformation to MDS, and AML have also been observed in patients treated with filgrastim products for SCN. Based on available data including a postmarketing surveillance study, the risk of developing MDS and AML appears to be confined to the subset of patients with congenital neutropenia. Abnormal cytogenetics and MDS have been associated with the eventual development of myeloid leukemia. The effect of filgrastim products on the development of abnormal cytogenetics and the effect of continued filgrastim products administration in patients with abnormal cytogenetics or MDS are unknown. Monitor patients for signs and symptoms of MDS/AML in these settings. If a patient with SCN develops abnormal cytogenetics or myelodysplasia‚ the risks and benefits of continuing ZARXIO should be carefully considered.

Patients with Breast and Lung Cancer

MDS and AML have been associated with the use of filgrastim products in conjunction with chemotherapy and/or radiotherapy in patients with breast and lung cancer. Monitor patients for signs and symptoms of MDS/AML in these settings.

5.9 Thrombocytopenia

Thrombocytopenia has been reported in patients receiving filgrastim products. Monitor platelet counts.

5.10 Leukocytosis

Patients with Cancer Receiving Myelosuppressive Chemotherapy

White blood cell counts of 100‚000/mm^3 or greater were observed in approximately 2% of patients receiving filgrastim at dosages above 5 mcg/kg/day. In patients with cancer receiving ZARXIO as an adjunct to myelosuppressive chemotherapy‚ to avoid the potential risks of excessive leukocytosis‚ it is recommended that ZARXIO therapy be discontinued if the ANC surpasses 10‚000/mm^3 after the chemotherapy-induced ANC nadir has occurred. Monitor CBCs at least twice weekly during therapy. Dosages of ZARXIO that increase the ANC beyond 10‚000/mm^3 may not result in any additional clinical benefit. In patients with cancer receiving myelosuppressive chemotherapy‚ discontinuation of filgrastim therapy usually resulted in a 50% decrease in circulating neutrophils within 1 to 2 days‚ with a return to pretreatment levels in 1 to 7 days.

Peripheral Blood Progenitor Cell Collection and Therapy

During the period of administration of ZARXIO for PBPC mobilization in patients with cancer, discontinue ZARXIO if the leukocyte count rises to > 100,000/mm^3.

5.11 Cutaneous Vasculitis

Cutaneous vasculitis has been reported in patients treated with filgrastim products. In most cases‚ the severity of cutaneous vasculitis was moderate or severe. Most of the reports involved patients with SCN receiving long-term filgrastim therapy. Hold ZARXIO therapy in patients with cutaneous vasculitis. ZARXIO may be started at a reduced dose when the symptoms resolve and the ANC has decreased.

5.12 Potential Effect on Malignant Cells

ZARXIO is a growth factor that primarily stimulates neutrophils. The granulocyte colony-stimulating factor (G‑CSF) receptor through which ZARXIO acts has also been found on tumor cell lines. The possibility that ZARXIO acts as a growth factor for any tumor type cannot be excluded. The safety of filgrastim products in chronic myeloid leukemia (CML) and myelodysplasia has not been established.

When ZARXIO is used to mobilize PBPC‚ tumor cells may be released from the marrow and subsequently collected in the leukapheresis product. The effect of reinfusion of tumor cells has not been well studied‚ and the limited data available are inconclusive.

5.13 Simultaneous Use with Chemotherapy and Radiation Therapy Not Recommended

The safety and efficacy of ZARXIO given simultaneously with cytotoxic chemotherapy have not been established. Because of the potential sensitivity of rapidly dividing myeloid cells to cytotoxic chemotherapy‚ do not use ZARXIO in the period 24 hours before through 24 hours after the administration of cytotoxic chemotherapy [see Dosage and Administration (2.2)].

The safety and efficacy of ZARXIO have not been evaluated in patients receiving concurrent radiation therapy. Avoid the simultaneous use of ZARXIO with chemotherapy and radiation therapy.

5.14 Nuclear Imaging

Increased hematopoietic activity of the bone marrow in response to growth factor therapy has been associated with transient positive bone-imaging changes. This should be considered when interpreting bone-imaging results.

5.15 Aortitis

Aortitis has been reported in patients receiving filgrastim products. It may occur as early as the first week after start of therapy. Manifestations may include generalized signs and symptoms such as fever, abdominal pain, malaise, back pain, and increased inflammatory markers (e.g., c-reactive protein and white blood cell count). Consider aortitis in patients who develop these signs and symptoms without known etiology. Discontinue ZARXIO if aortitis is suspected.

6 ADVERSE REACTIONS

The following serious adverse reactions are discussed in greater detail in other sections of the labeling:

- Splenic Rupture [see Warnings and Precautions (5.1)]
- Acute Respiratory Distress Syndrome [see Warnings and Precautions (5.2)]
- Serious Allergic Reactions [see Warnings and Precautions (5.3)]
- Sickle Cell Disorders [see Warnings and Precautions (5.4)]
- Glomerulonephritis [see Warnings and Precautions (5.5)]
- Alveolar Hemorrhage and Hemoptysis [see Warnings and Precautions (5.6)]
- Capillary Leak Syndrome [see Warnings and Precautions (5.7)]
- Myelodysplastic Syndrome [see Warnings and Precautions (5.8)]
- Acute Myeloid Leukemia [see Warnings and Precautions (5.8)]
- Thrombocytopenia [see Warnings and Precautions (5.9)]
- Leukocytosis [see Warnings and Precautions (5.10)]
- Cutaneous Vasculitis [see Warnings and Precautions (5.11)]
- Aortitis [see Warnings and Precautions (5.15)]

6.1 Clinical Trials Experience

Because clinical trials are conducted under widely varying conditions, adverse reaction rates observed in the clinical trials of a drug cannot be directly compared with rates in the clinical trials of another drug and may not reflect the rates observed in clinical practice.

Adverse Reactions in Patients with Cancer Receiving Myelosuppressive Chemotherapy

The following adverse reaction data in Table 2 are from three randomized, placebo-controlled studies in patients with:

- small cell lung cancer receiving standard dose chemotherapy with cyclophosphamide‚ doxorubicin‚ and etoposide (Study 1)
- small cell lung cancer receiving ifosfamide, doxorubicin‚ and etoposide (Study 2), and
- non-Hodgkin’s lymphoma (NHL) receiving doxorubicin, cyclophosphamide, vindesine, bleomycin, methylprednisolone, and methotrexate (“ACVBP”) or mitoxantrone, ifosfamide, mitoguazone, teniposide, methotrexate, folinic acid, methylprednisolone, and methotrexate (“VIM3”) (Study 3).

A total of 451 patients were randomized to receive subcutaneous filgrastim 230 mcg/m^2 (Study 1), 240 mcg/m^2 (Study 2) or 4 or 5 mcg/kg/day (Study 3) (n=294) or placebo (n=157). The patients in these studies were median age 61 (range 29 to 78) years and 64% were male. The ethnicity was 95% Caucasian, 4% African American, and 1% Asian.

Table 2. Adverse Reactions in Patients with Cancer Receiving Myelosuppressive Chemotherapy (With ≥ 5% Higher Incidence in Filgrastim Compared to Placebo)

System Organ Class Preferred Term | Filgrastim (N=294) | Placebo (N=157)
Blood and lymphatic system disorders
Thrombocytopenia | 38% | 29%
Gastrointestinal disorders
Nausea | 43% | 32%
General disorders and administration site conditions
Pyrexia | 48% | 29%
Chest pain | 13% | 6%
Pain | 12% | 6%
Fatigue | 20% | 10%
Musculoskeletal and connective tissue disorders
Back pain | 15% | 8%
Arthralgia | 9% | 2%
Bone pain | 11% | 6%
Pain in extremity [Percent difference (Filgrastim – Placebo) was 4%.] | 7% | 3%
Nervous system disorders
Dizziness | 14% | 3%
Respiratory, thoracic and mediastinal disorders
Cough | 14% | 8%
Dyspnea | 13% | 8%
Skin and subcutaneous tissue disorders
Rash | 14% | 5%
Investigations
Blood lactate dehydrogenase increased | 6% | 1%
Blood alkaline phosphatase increased | 6% | 1%

Adverse events with ≥ 5% higher incidence in filgrastim patients compared to placebo and associated with the sequelae of the underlying malignancy or cytotoxic chemotherapy delivered included anemia, constipation, diarrhea, oral pain, vomiting, asthenia, malaise, edema peripheral, hemoglobin decreased, decreased appetite, oropharyngeal pain, and alopecia.

Adverse Reactions in Patients with Acute Myeloid Leukemia

Adverse reaction data below are from a randomized, double-blind, placebo-controlled study in patients with AML (Study 4) who received an induction chemotherapy regimen of intravenous daunorubicin days 1, 2, and 3; cytosine arabinoside days 1 to 7; and etoposide days 1 to 5 and up to 3 additional courses of therapy (induction 2, and consolidation 1, 2) of intravenous daunorubicin, cytosine arabinoside, and etoposide. The safety population included 518 patients randomized to receive either 5 mcg/kg/day filgrastim (n=257) or placebo (n=261). The median age was 54 (range 16 to 89) years and 54% were male.

Adverse reactions with ≥ 2% higher incidence in filgrastim patients compared to placebo included epistaxis, back pain, pain in extremity, erythema, and rash maculo-papular.

Adverse events with ≥ 2% higher incidence in filgrastim patients compared to placebo and associated with the sequelae of the underlying malignancy or cytotoxic chemotherapy included diarrhea, constipation, and transfusion reaction.

Adverse Reactions in Patients with Cancer Undergoing Bone Marrow Transplantation

The following adverse reaction data are from one randomized, no treatment-controlled study in patients with acute lymphoblastic leukemia or lymphoblastic lymphoma receiving high-dose chemotherapy (cyclophosphamide or cytarabine, and melphalan) and total body irradiation (Study 5) and one randomized, no treatment-controlled study in patients with Hodgkin’s disease (HD) and NHL undergoing high-dose chemotherapy and autologous bone marrow transplantation (Study 6). Patients receiving autologous bone marrow transplantation only were included in the analysis. A total of 100 patients received either 30 mcg/kg/day as a 4-hour infusion (Study 5) or 10 mcg/kg/day or 30 mcg/kg/day as a 24-hour infusion (Study 6) filgrastim (n=72), no treatment control or placebo (n=28). The median age was 30 (range 15 to 57) years, 57% were male.

Adverse reactions with ≥ 5% higher incidence in filgrastim patients compared to patients receiving no filgrastim included rash and hypersensitivity.

Adverse reactions in patients receiving intensive chemotherapy followed by autologous BMT with ≥ 5% higher incidence in filgrastim patients compared to patients receiving no filgrastim included thrombocytopenia, anemia, hypertension, sepsis, bronchitis, and insomnia.

Adverse Reactions in Patients with Cancer Undergoing Autologous Peripheral Blood Progenitor Cell Collection

The adverse reaction data in Table 3 are from a series of 7 trials in patients with cancer undergoing mobilization of autologous peripheral blood progenitor cells for collection by leukapheresis. Patients (n=166) in all these trials underwent a similar mobilization/collection regimen: filgrastim was administered for 6 to 8 days‚ in most cases the apheresis procedure occurred on days 5‚ 6, and 7. The dosage of filgrastim ranged between 5 to 30 mcg/kg/day and was administered subcutaneously by injection or continuous infusion. The median age was 39 (range 15 to 67) years, and 48% were male.

Table 3. Adverse Reactions in Patients with Cancer Undergoing Autologous PBPC in the Mobilization Phase (≥ 5% Incidence in Filgrastim Patients)

System Organ Class Preferred Term | Mobilization Phase (N=166)
Musculoskeletal and connective tissue disorders
Bone pain | 30%
General disorders and administration site conditions
Pyrexia | 16%
Investigations
Blood alkaline phosphatase increased | 11%
Nervous system disorders
Headache | 10%

Adverse Reactions in Patients with Severe Chronic Neutropenia

The following adverse reaction data were identified in a randomized, controlled study in patients with SCN receiving filgrastim (Study 7). 123 patients were randomized to a 4-month observation period followed by subcutaneous filgrastim treatment or immediate subcutaneous filgrastim treatment. The median age was 12 years (range 7 months to 76 years) and 46% were male. The dosage of filgrastim was determined by the category of neutropenia.

Initial dosage of filgrastim:

- Idiopathic neutropenia: 3.6 mcg/kg/day
- Cyclic neutropenia: 6 mcg/kg/day
- Congenital neutropenia: 6 mcg/kg/day divided 2 times per day

The dosage was increased incrementally to 12 mcg/kg/day divided 2 times per day if there was no response.

Adverse reactions with ≥ 5% higher incidence in filgrastim patients compared to patients receiving no filgrastim included arthralgia, bone pain, back pain, muscle spasms, musculoskeletal pain, pain in extremity, splenomegaly, anemia, upper respiratory tract infection, and urinary tract infection (upper respiratory tract infection and urinary tract infection were higher in the filgrastim arm, total infection related events were lower in filgrastim-treated patients), epistaxis, chest pain, diarrhea, hypoesthesia, and alopecia.

6.2 Postmarketing Experience

The following adverse reactions have been identified during post-approval use of filgrastim products. Because these reactions are reported voluntarily from a population of uncertain size, it is not always possible to reliably estimate their frequency or establish a causal relationship to drug exposure.

- splenic rupture and splenomegaly (enlarged spleen) [see Warnings and Precautions (5.1)]
- acute respiratory distress syndrome [see Warnings and Precautions (5.2)]
- anaphylaxis [see Warnings and Precautions (5.3)]
- sickle cell disorders [see Warnings and Precautions (5.4)]
- glomerulonephritis [see Warnings and Precautions (5.5)]
- alveolar hemorrhage and hemoptysis [see Warnings and Precautions (5.6)]
- capillary leak syndrome [see Warnings and Precautions (5.7)]
- leukocytosis [see Warnings and Precautions (5.10)]
- cutaneous vasculitis [see Warnings and Precautions (5.11)]
- Sweet’s syndrome (acute febrile neutrophilic dermatosis)
- decreased bone density and osteoporosis in pediatric patients receiving chronic treatment with filgrastim products
- myelodysplastic syndrome (MDS) and acute myeloid leukemia (AML) in patients with breast and lung cancer receiving chemotherapy and/or radiotherapy [see Warnings and Precautions (5.8)]
- aortitis [see Warnings and Precautions (5.15)]
- extramedullary hematopoiesis

8 USE IN SPECIFIC POPULATIONS

8.1 Pregnancy

Risk Summary

Available data from published studies, including several observational studies of pregnancy outcomes in women exposed to filgrastim products and those who were unexposed, have not established an association with filgrastim product use during pregnancy and major birth defects, miscarriage, or adverse maternal or fetal outcomes (see Data). Reports in the scientific literature have described transplacental passage of filgrastim in pregnant women when administered ≤ 30 hours prior to preterm delivery (≤ 30 weeks gestation). In animal reproduction studies, effects of filgrastim on prenatal development have been studied in rats and rabbits. No malformations were observed in either species. No maternal or fetal effects were observed in pregnant rats at doses up to 58 times the human doses. Filgrastim has been shown to have adverse effects in pregnant rabbits at doses 2 to 10 times higher than the human doses (see Data).

The estimated background risk of major birth defects and miscarriage for the indicated population is unknown. All pregnancies have a background risk of birth defect, loss, or other adverse outcomes. In the U.S. general population, the estimated background risks of major birth defects and miscarriage in clinically recognized pregnancies is 2-4% and 15- 20%, respectively.

Data

Human Data

Several observational studies based on the Severe Chronic Neutropenia International Registry (SCNIR) described pregnancy outcomes in women with severe chronic neutropenia (SCN) who were exposed to filgrastim products during pregnancy and women with SCN who were unexposed. No major differences were seen between treated and untreated women with respect to pregnancy outcome (including miscarriage and preterm labor), newborn complications (including birth weight), and infections. Methodological limitations of these studies include small sample size and lack of generalizability due to the underlying maternal condition.

Animal Data

Effects of filgrastim on prenatal development have been studied in rats and rabbits. No malformations were observed in either species. Filgrastim has been shown to have adverse effects in pregnant rabbits at doses 2 to 10 times higher than the human doses. In pregnant rabbits showing signs of maternal toxicity, reduced embryo-fetal survival (at 20 and 80 mcg/kg/day) and increased abortions (at 80 mcg/kg/day) were observed. In pregnant rats, no maternal or fetal effects were observed at doses up to 575 mcg/kg/day, which is approximately 58 times higher than the human dose of 10 mcg/kg/day.

Offspring of rats administered filgrastim during the peri-natal and lactation periods exhibited a delay in external differentiation and growth retardation (≥ 20 mcg/kg/day) and slightly reduced survival rate (100 mcg/kg/day).

8.2 Lactation

Risk Summary

There is published literature documenting transfer of filgrastim into human milk. There are a few case reports describing the use of filgrastim in breastfeeding mothers with no adverse effects noted in the infants. There are no data on the effects of filgrastim products on milk production. Other filgrastim products are secreted poorly into breast milk, and filgrastim products are not absorbed orally by neonates. The developmental and health benefits of breastfeeding should be considered along with the mother’s clinical need for ZARXIO and any potential adverse effects on the breastfed child from ZARXIO or from the underlying maternal condition.

8.4 Pediatric Use

ZARXIO prefilled syringe with BD UltraSafe Passive® Needle Guard may not accurately measure volumes less than 0.3 mL due to the needle spring mechanism design. Therefore, the direct administration of a volume less than 0.3 mL using ZARXIO prefilled syringe is not recommended due to the potential for dosing errors. For direct administration of doses less than 0.3 mL (180 mcg) use ZARXIO single-dose vial.

In patients with cancer receiving myelosuppressive chemotherapy‚ 15 pediatric patients median age 2.6 (range 1.2 to 9.4) years with neuroblastoma were treated with myelosuppressive chemotherapy (cyclophosphamide‚ cisplatin‚ doxorubicin‚ and etoposide) followed by subcutaneous filgrastim at doses of 5, 10, or 15 mcg/kg/day for 10 days (n=5/dose) (Study 8). The pharmacokinetics of filgrastim in pediatric patients after chemotherapy are similar to those in adults receiving the same weight-normalized doses, suggesting no age-related differences in the pharmacokinetics of filgrastim. In this population‚ filgrastim was well tolerated. There was one report of palpable splenomegaly and one report of hepatosplenomegaly associated with filgrastim therapy; however‚ the only consistently reported adverse event was musculoskeletal pain‚ which is no different from the experience in the adult population.

The safety and effectiveness of ZARXIO have been established in pediatric patients with SCN [see Clinical Studies (14.5)]. In a phase 3 study (Study 7) to assess the safety and efficacy of filgrastim in the treatment of SCN, 123 patients with a median age of 12 years (range 7 months to 76 years) were studied. Of the 123 patients, 12 were infants (7 months to 2 years of age), 49 were children (2 to 12 years of age), and 9 were adolescents (12 to 16 years of age). Additional information is available from a SCN postmarketing surveillance study, which includes long-term follow-up of patients in the clinical studies and information from additional patients who entered directly into the postmarketing surveillance study. Of the 731 patients in the surveillance study, 429 were pediatric patients < 18 years of age (range 0.9 to 17) [see Indications and Usage (1.5), Dosage and Administration (2.6), and Clinical Studies (14.5)].

Long-term follow-up data from the postmarketing surveillance study suggest that height and weight are not adversely affected in patients who received up to 5 years of filgrastim treatment. Limited data from patients who were followed in the phase 3 study for 1.5 years did not suggest alterations in sexual maturation or endocrine function.

Pediatric patients with congenital types of neutropenia (Kostmann’s syndrome, congenital agranulocytosis, or Schwachman-Diamond syndrome) have developed cytogenetic abnormalities and have undergone transformation to MDS and AML while receiving chronic filgrastim treatment. The relationship of these events to filgrastim product administration is unknown [see Warnings and Precautions (5.8) and Adverse Reactions (6)].

The use of ZARXIO to increase survival in pediatric patients acutely exposed to myelosuppressive doses of radiation is based on studies of filgrastim conducted in animals and clinical data supporting the use of filgrastim in other approved indications [see Dosage and Administration (2.1 to 2.4) and Clinical Studies (14.6)].

8.5 Geriatric Use

Among 855 subjects enrolled in 3 randomized, placebo-controlled trials of filgrastim treated-patients receiving myelosuppressive chemotherapy, there were 232 subjects age 65 or older, and 22 subjects age 75 or older. No overall differences in safety or effectiveness were observed between these subjects and younger subjects.

Clinical studies of filgrastim in other approved indications (i.e., BMT recipients, PBPC mobilization, and SCN) did not include sufficient numbers of subjects aged 65 and older to determine whether elderly subjects respond differently from younger subjects.

10 OVERDOSAGE

The maximum tolerated dose of filgrastim products has not been determined. In filgrastim clinical trials of patients with cancer receiving myelosuppressive chemotherapy‚ WBC counts > 100‚000/mm^3 have been reported in less than 5% of patients‚ but were not associated with any reported adverse clinical effects. Patients in the BMT studies received up to 138 mcg/kg/day without toxic effects‚ although there was a flattening of the dose response curve above daily doses of greater than 10 mcg/kg/day.

11 DESCRIPTION

Filgrastim-sndz is a 175 amino acid human granulocyte colony-stimulating factor (G-CSF) manufactured by recombinant DNA technology. Filgrastim-sndz is produced by Escherichia coli (E coli) bacteria into which has been inserted the human granulocyte colony-stimulating factor gene. Filgrastim-sndz has a molecular weight of 18‚800 daltons. The protein has an amino acid sequence that is identical to the natural sequence predicted from human DNA sequence analysis‚ except for the addition of an N-terminal methionine necessary for expression in E coli. Because filgrastim-sndz is produced in E coli‚ the product is non-glycosylated and thus differs from G-CSF isolated from a human cell.

ZARXIO (filgrastim-sndz) injection is a sterile‚ clear‚ colorless to slightly yellowish‚ preservative-free liquid containing filgrastim-sndz at a specific activity of 1 x 10^8 U/mg (as measured by a proliferation assay). The product is available in single-dose vials and single-dose prefilled syringes for subcutaneous or intravenous use. The single-dose vials contain either 300 mcg/mL or 480 mcg/1.6 mL of filgrastim-sndz. The single-dose prefilled syringes contain either 300 mcg/0.5 mL or 480 mcg/0.8 mL of filgrastim-sndz. The ZARXIO drug product has a pH of 4.4. See Table 4 below for product composition of each single-dose vial and prefilled syringe.

Table 4. Product Composition

 | 300 mcg/mL Vial | 480 mcg/1.6 mL Vial | 300 mcg/0.5 mL Syringe | 480 mcg/0.8 mL Syringe
Filgrastim-sndz | 300 mcg | 480 mcg | 300 mcg | 480 mcg
Glutamic Acid | 1.471 mg | 2.354 mg | 0.736 mg | 1.178 mg
Polysorbate 80 | 0.04 mg | 0.064 mg | 0.02 mg | 0.032 mg
Sorbitol | 50 mg | 80 mg | 25 mg | 40 mg
Sodium hydroxide | q.s. | q.s. | q.s. | q.s.
Water for Injection USP q.s. ad* | ad 1 mL | ad 1.6 mL | ad 0.5 mL | ad 0.8 mL

*q.s.: quantity sufficient to make

12 CLINICAL PHARMACOLOGY

12.1 Mechanism of Action

Colony-stimulating factors are glycoproteins which act on hematopoietic cells by binding to specific cell surface receptors and stimulating proliferation‚ differentiation commitment‚ and some end-cell functional activation.

Endogenous G-CSF is a lineage-specific colony-stimulating factor that is produced by monocytes‚ fibroblasts, and endothelial cells. G-CSF regulates the production of neutrophils within the bone marrow and affects neutrophil progenitor proliferation‚ differentiation, and selected end-cell functions (including enhanced phagocytic ability‚ priming of the cellular metabolism associated with respiratory burst‚ antibody-dependent killing, and the increased expression of some cell surface antigens). G-CSF is not species-specific and has been shown to have minimal direct in vivo or in vitro effects on the production or activity of hematopoietic cell types other than the neutrophil lineage.

12.2 Pharmacodynamics

In phase 1 studies involving 96 patients with various nonmyeloid malignancies‚ administration of filgrastim resulted in a dose-dependent increase in circulating neutrophil counts over the dose range of 1 to 70 mcg/kg/day. This increase in neutrophil counts was observed whether filgrastim was administered intravenous (1 to 70 mcg/kg twice daily)‚ subcutaneous (1 to 3 mcg/kg once daily)‚ or by continuous subcutaneous infusion (3 to 11 mcg/kg/day). With discontinuation of filgrastim therapy‚ neutrophil counts returned to baseline in most cases within 4 days. Isolated neutrophils displayed normal phagocytic (measured by zymosan-stimulated chemiluminescence) and chemotactic (measured by migration under agarose using N-formyl-methionyl-leucyl‑phenylalanine [fMLP] as the chemotaxin) activity in vitro.

The absolute monocyte count was reported to increase in a dose-dependent manner in most patients receiving filgrastim; however‚ the percentage of monocytes in the differential count remained within the normal range. Absolute counts of both eosinophils and basophils did not change and were within the normal range following administration of filgrastim. Increases in lymphocyte counts following filgrastim administration have been reported in some normal subjects and patients with cancer.

White blood cell (WBC) differentials obtained during clinical trials have demonstrated a shift towards earlier granulocyte progenitor cells (left shift)‚ including the appearance of promyelocytes and myeloblasts‚ usually during neutrophil recovery following the chemotherapy-induced nadir. In addition‚ Dohle bodies‚ increased granulocyte granulation‚ and hypersegmented neutrophils have been observed. Such changes were transient and were not associated with clinical sequelae, nor were they necessarily associated with infection.

12.3 Pharmacokinetics

Filgrastim products exhibit nonlinear pharmacokinetics. Clearance is dependent on filgrastim product concentration and neutrophil count: G-CSF receptor-mediated clearance is saturated by high concentration of filgrastim products and is diminished by neutropenia. In addition, filgrastim products are cleared by the kidney.

Subcutaneous administration of 3.45 mcg/kg and 11.5 mcg/kg of filgrastim resulted in maximum serum concentrations of 4 and 49 ng/mL‚ respectively‚ within 2 to 8 hours. After intravenous administration, the volume of distribution averaged 150 mL/kg and the elimination half-life was approximately 3.5 hours in both normal subjects and subjects with cancer. Clearance rates of filgrastim were approximately 0.5 to 0.7 mL/minute/kg. Single parenteral doses or daily intravenous doses‚ over a 14-day period‚ resulted in comparable half-lives. The half-lives were similar for intravenous administration (231 minutes‚ following doses of 34.5 mcg/kg) and for subcutaneous administration (210 minutes‚ following filgrastim dosages of 3.45 mcg/kg). Continuous 24-hour intravenous infusions of 20 mcg/kg over an 11 to 20-day period produced steady-state serum concentrations of filgrastim with no evidence of drug accumulation over the time period investigated. The absolute bioavailability of filgrastim after subcutaneous administration is 60% to 70%.

Specific Populations

Patients Acutely Exposed to Myelosuppressive Doses of Radiation

The pharmacokinetics of filgrastim products are not available in patients acutely exposed to myelosuppressive doses of radiation. Based on limited pharmacokinetics data in irradiated non-human primates, the area under the time-concentration curve (AUC), reflecting the exposure to filgrastim in non-human primates at 10 mcg/kg dose of filgrastim, appears to be similar to that in humans at 5 mcg/kg. Simulations conducted using the population pharmacokinetic model indicates that the exposures to filgrastim at a filgrastim dose of 10 mcg/kg in patients acutely exposed to myelosuppressive doses of radiation are expected to exceed the exposures at a dose of 10 mcg/kg in irradiated non-human primates.

Pediatric Patients

The pharmacokinetics of filgrastim in pediatric patients after chemotherapy are similar to those in adult patients receiving the same weight-normalized doses, suggesting no age-related differences in the pharmacokinetics of filgrastim products [see Use in Specific Populations (8.4)].

Renal Impairment

In a study with healthy volunteers, subjects with moderate renal impairment, and subjects with end stage renal disease (n=4 per group), higher serum concentrations were observed in subjects with end-stage renal disease. However, dose adjustment in patients with renal impairment is not necessary.

Hepatic Impairment

Pharmacokinetics and pharmacodynamics of filgrastim are similar between subjects with hepatic impairment and healthy subjects (n=12/group). The study included 10 subjects with mild hepatic impairment (Child-Pugh Class A) and 2 subjects with moderate hepatic impairment (Child-Pugh Class B). Therefore, dose adjustment for ZARXIO in patients with hepatic impairment is not necessary.

12.6 Immunogenicity

The observed incidence of anti-drug antibodies is highly dependent on the sensitivity and specificity of the assay. Differences in assay methods preclude meaningful comparisons of the incidence of anti-drug antibodies in the studies described below with the incidence of anti-drug antibodies in other studies, including those of filgrastim or of other filgrastim products.

While available data suggest that a small proportion of patients developed binding antibodies to filgrastim products, the nature and specificity of these antibodies has not been adequately studied. In clinical studies using filgrastim, the incidence of antibodies binding to filgrastim was 3% (11/333). In these 11 patients, no evidence of a neutralizing response was observed using a cell based bioassay. Because of the low occurrence of anti-drug antibodies, the effect of these antibodies on the pharmacokinetics, pharmacodynamics, safety, and/or effectiveness of filgrastim products is unknown.

Cytopenias resulting from an antibody response to exogenous growth factors have been reported on rare occasions in patients treated with other recombinant growth factors.

13 NONCLINICAL TOXICOLOGY

13.1 Carcinogenesis, Mutagenesis, Impairment of Fertility

The carcinogenic potential of filgrastim products has not been studied. Filgrastim failed to induce bacterial gene mutations in either the presence or absence of a drug metabolizing enzyme system. Filgrastim had no observed effect on the fertility of male or female rats at doses up to 500 mcg/kg.

13.2 Animal Toxicology and Pharmacology

Filgrastim was administered to monkeys‚ dogs‚ hamsters‚ rats‚ and mice as part of a nonclinical toxicology program, which included studies up to 1-year duration.

In the repeated-dose studies‚ changes observed were attributable to the expected pharmacological actions of filgrastim (i.e.‚ dose-dependent increases in white blood cell counts‚ increased circulating segmented neutrophils‚ and increased myeloid: erythroid ratio in bone marrow). Histopathologic examination of the liver and spleen revealed evidence of ongoing extramedullary granulopoiesis, and dose-related increases in spleen weight were seen in all species. These changes all reversed after discontinuation of treatment.

14 CLINICAL STUDIES

14.1 Patients with Cancer Receiving Myelosuppressive Chemotherapy

The safety and efficacy of filgrastim to decrease the incidence of infection‚ as manifested by febrile neutropenia‚ in patients with nonmyeloid malignancies receiving myelosuppressive anti-cancer drugs were established in a randomized‚ double-blind‚ placebo-controlled trial conducted in patients with small cell lung cancer (Study 1).

In Study 1, patients received up to 6 cycles of intravenous chemotherapy including intravenous cyclophosphamide and doxorubicin on day 1; and etoposide on days 1, 2, and 3 of 21 day cycles. Patients were randomized to receive filgrastim (n=99) at a dose of 230 mcg/m^2 (4 to 8 mcg/kg/day) or placebo (n=111). Study drug was administered subcutaneously daily beginning on day 4, for a maximum of 14 days. A total of 210 patients were evaluable for efficacy and 207 were evaluable for safety. The demographic and disease characteristics were balanced between arms with a median age of 62 (range 31 to 80) years; 64% males; 89% Caucasian; 72% extensive disease and 28% limited disease.

The main efficacy endpoint was the incidence of febrile neutropenia. Febrile neutropenia was defined as an ANC < 1,000/mm^3 and temperature > 38.2°C. Treatment with filgrastim resulted in a clinically and statistically significant reduction in the incidence of infection‚ as manifested by febrile neutropenia, 40% for filgrastim-treated patients and 76% for placebo-treated patients (p < 0.001). There were also statistically significant reductions in the incidence and overall duration of infection manifested by febrile neutropenia; the incidence, severity and duration of severe neutropenia (ANC < 500/mm^3); the incidence and overall duration of hospital admissions; and the number of reported days of antibiotic use.

14.2 Patients with Acute Myeloid Leukemia Receiving Induction or Consolidation Chemotherapy

The safety and efficacy of filgrastim to reduce the time to neutrophil recovery and the duration of fever, following induction or consolidation chemotherapy treatment of patients with acute myeloid leukemia (AML) was established in a randomized, double-blind‚ placebo-controlled‚ multi-center trial in patients with newly diagnosed, de novo AML (Study 4).

In Study 4 the initial induction therapy consisted of intravenous daunorubicin days 1, 2, and 3; cytosine arabinoside days 1 to 7; and etoposide days 1 to 5. Patients were randomized to receive subcutaneous filgrastim (n=259) at a dose of 5 mcg/kg/day or placebo (n=262) from 24 hours after the last dose of chemotherapy until neutrophil recovery (ANC ≥1,000/mm^3 for 3 consecutive days or ≥ 10,000/mm^3 for 1 day) or for a maximum of 35 days. The demographic and disease characteristics were balanced between arms with a median age of 54 (range 16 to 89) years; 54% males; initial white blood cell count (65% <25,000 /mm^3 and 27% > 100,000/mm^3); 29% unfavorable cytogenetics.

The main efficacy endpoint was median duration of severe neutropenia defined as neutrophil count < 500/mm^3. Treatment with filgrastim resulted in a clinically and statistically significant reduction in median number of days of severe neutropenia, filgrastim-treated patients 14 days, placebo-treated patients 19 days (p=0.0001: difference of 5 days (95% CI: -6.0, -4.0)). There was a reduction in the median duration of intravenous antibiotic use, filgrastim-treated patients: 15 days versus placebo-treated patients: 18.5 days; a reduction in the median duration of hospitalization, filgrastim-treated patients: 20 days versus placebo-treated patients: 25 days.

There were no statistically significant differences between the filgrastim and the placebo groups in complete remission rate (69% - filgrastim, 68% - placebo), median time to progression of all randomized patients (165 days - filgrastim, 186 days - placebo), or median overall survival (380 days - filgrastim, 425 days - placebo).

14.3 Patients with Cancer Undergoing Bone Marrow Transplantation

The safety and efficacy of filgrastim to reduce the duration of neutropenia in patients with nonmyeloid malignancies undergoing myeloablative chemotherapy followed by autologous bone marrow transplantation was evaluated in 2 randomized controlled trials of patients with lymphoma (Study 6 and Study 9). The safety and efficacy of filgrastim to reduce the duration of neutropenia in patients undergoing myeloablative chemotherapy followed by allogeneic bone marrow transplantation was evaluated in a randomized placebo-controlled trial (Study 10).

In Study 6, patients with Hodgkin’s disease received a preparative regimen of intravenous cyclophosphamide, etoposide, and BCNU (“CVP”), and patients with non-Hodgkin’s lymphoma received intravenous BCNU, etoposide, cytosine arabinoside and melphalan (“BEAM”). There were 54 patients randomized 1:1:1 to control, filgrastim 10 mcg/kg/day, and filgrastim 30 mcg/kg/day as a 24-hour continuous infusion starting 24-hours after bone marrow infusion for a maximum of 28 days. The median age was 33 (range 17 to 57) years; 56% males; 69% Hodgkin’s disease and 31% non-Hodgkin’s lymphoma.

The main efficacy endpoint was duration of severe neutropenia ANC < 500/mm^3. A statistically significant reduction in the median number of days of severe neutropenia (ANC < 500/mm^3) occurred in the filgrastim-treated groups versus the control group (23 days in the control group‚ 11 days in the 10 mcg/kg/day group‚ and 14 days in the 30 mcg/kg/day group [11 days in the combined treatment groups‚ p=0.004]).

In Study 9, patients with Hodgkin’s disease and non-Hodgkin’s lymphoma received a preparative regimen of intravenous cyclophosphamide, etoposide, and BCNU (“CVP”). There were 43 evaluable patients randomized to continuous subcutaneous infusion filgrastim 10 mcg/kg/day (n=19), filgrastim 30 mcg/kg/day (n=10) and no treatment (n=14) starting the day after marrow infusion for a maximum of 28 days. The median age was 33 (range 17 to 56) years; 67% males; 28% Hodgkin’s disease and 72% non-Hodgkin’s lymphoma.

The main efficacy endpoint was duration of severe neutropenia. There was statistically significant reduction in the median number of days of severe neutropenia (ANC < 500/mm^3) in the filgrastim-treated groups versus the control group (21.5 days in the control group versus 10 days in the filgrastim-treated groups, p < 0.001). The number of days of febrile neutropenia was also reduced significantly in this study (13.5 days in the control group versus 5 days in the filgrastim-treated groups‚ p < 0.0001).

In Study 10, 70 patients scheduled to undergo bone marrow transplantation for multiple underlying conditions using multiple preparative regimens were randomized to receive filgrastim 300 mcg/m^2/day (n=33) or placebo (n=37) days 5 through 28 after marrow infusion. The median age was 18 (range 1 to 45) years, 56% males. The underlying disease was: 67% hematologic malignancy, 24% aplastic anemia, 9% other. A statistically significant reduction in the median number of days of severe neutropenia occurred in the treated group versus the control group (19 days in the control group and 15 days in the treatment group‚ p < 0.001) and time to recovery of ANC to ≥ 500/mm^3 (21 days in the control group and 16 days in the treatment group‚ p < 0.001).

14.4 Patients Undergoing Autologous Peripheral Blood Progenitor Cell Collection and Therapy

The safety and efficacy of filgrastim to mobilize autologous peripheral blood progenitor cells for collection by leukapheresis was supported by the experience in uncontrolled trials, and a randomized trial comparing hematopoietic stem cell rescue using filgrastim-mobilized autologous peripheral blood progenitor cells to autologous bone marrow (Study 11). Patients in all these trials underwent a similar mobilization/collection regimen: filgrastim was administered for 6 to 7 days‚ in most cases the apheresis procedure occurred on days 5‚ 6, and 7. The dose of filgrastim ranged between 10 to 24 mcg/kg/day and was administered subcutaneously by injection or continuous intravenous infusion.

Engraftment was evaluated in 64 patients who underwent transplantation using filgrastim-mobilized autologous hematopoietic progenitor cells in uncontrolled trials. Two of the 64 patients (3%) did not achieve the criteria for engraftment as defined by a platelet count ≥ 20‚000/mm^3 by day 28. In clinical trials of filgrastim for the mobilization of hematopoietic progenitor cells‚ filgrastim was administered to patients at doses between 5 to 24 mcg/kg/day after reinfusion of the collected cells until a sustainable ANC (≥ 500/mm^3) was reached. The rate of engraftment of these cells in the absence of filgrastim post transplantation has not been studied.

Study 11 was a randomized, unblinded study of patients with Hodgkin’s disease or non-Hodgkin’s lymphoma undergoing myeloablative chemotherapy‚ 27 patients received filgrastim-mobilized autologous hematopoietic progenitor cells and 31 patients received autologous bone marrow. The preparative regimen was intravenous BCNU, etoposide, cytosine arabinoside and melphalan (“BEAM”). Patients received daily filgrastim 24 hours after stem cell infusion at a dose of 5 mcg/kg/day. The median age was 33 (range 1 to 59) years; 64% males; 57% Hodgkin’s disease and 43% non-Hodgkin’s lymphoma. The main efficacy endpoint was number of days of platelet transfusions. Patients randomized to filgrastim-mobilized autologous peripheral blood progenitor cells compared to autologous bone marrow had significantly fewer days of platelet transfusions (median 6 vs 10 days).

14.5 Patients with Severe Chronic Neutropenia

The safety and efficacy of filgrastim to reduce the incidence and duration of sequelae of neutropenia (that is fever‚ infections, oropharyngeal ulcers) in symptomatic adult and pediatric patients with congenital neutropenia‚ cyclic neutropenia‚ or idiopathic neutropenia was established in a randomized controlled trial conducted in patients with severe neutropenia (Study 7).

Patients eligible for Study 7 had a history of severe chronic neutropenia documented with an ANC < 500/mm^3 on three occasions during a 6-month period, or in patients with cyclic neutropenia 5 consecutive days of ANC < 500/mm^3 per cycle. In addition, patients must have experienced a clinically significant infection during the previous 12 months. Patients were randomized to a 4-month observation period followed by filgrastim treatment or immediate filgrastim treatment. The median age was 12 years (range 7 months to 76 years); 46% males; 34% idiopathic, 17% cyclic and 49% congenital neutropenia. Filgrastim was administered subcutaneously. The dose of filgrastim was determined by the category of neutropenia.

Initial dose of filgrastim:

- Idiopathic neutropenia: 3.6 mcg/kg/day
- Cyclic neutropenia: 6 mcg/kg/day
- Congenital neutropenia: 6 mcg/kg/day divided 2 times per day

The dose was increased incrementally to 12 mcg/kg/day divided 2 times per day if there was no response.

The main efficacy endpoint was response to filgrastim treatment. ANC response from baseline (< 500/mm^3) was defined as follows:

- Complete response: median ANC > 1,500/mm^3
- Partial response: median ANC ≥ 500/mm^3 and ≤ 1,500/mm^3 with a minimum increase of 100%
- No response: median ANC < 500/mm^3

There were 112 of 123 patients who demonstrated a complete or partial response to filgrastim treatment.

Additional efficacy endpoints included a comparison between patients randomized to 4 months of observation and patients receiving filgrastim of the following parameters:

- incidence of infection
- incidence of fever
- duration of fever
- incidence, duration, and severity of oropharyngeal ulcers
- number of days of antibiotic use

The incidence for each of these 5 clinical parameters was lower in the filgrastim arm compared to the control arm for cohorts in each of the 3 major diagnostic categories. An analysis of variance showed no significant interaction between treatment and diagnosis‚ suggesting that efficacy did not differ substantially in the different diseases. Although filgrastim substantially reduced neutropenia in all patient groups‚ in patients with cyclic neutropenia‚ cycling persisted but the period of neutropenia was shortened to 1 day.

14.6 Patients Acutely Exposed to Myelosuppressive Doses of Radiation (Hematopoietic Syndrome of Acute Radiation Syndrome)

Efficacy studies of filgrastim products could not be conducted in humans with acute radiation syndrome for ethical and feasibility reasons. Approval of this indication was based on efficacy studies conducted in animals and data supporting the use of filgrastim for other approved indications [see Dosage and Administration (2.1 to 2.4)].

Because of the uncertainty associated with extrapolating animal efficacy data to humans, the selection of human dose for ZARXIO is aimed at providing exposures to filgrastim that exceed those observed in animal efficacy studies. The 10 mcg/kg daily dose is selected for humans exposed to myelosuppressive doses of radiation because the exposure associated with such a dose is expected to exceed the exposure associated with a 10 mcg/kg dose in non-human primates [see Clinical Pharmacology (12.3)]. The safety of filgrastim at a daily dose of 10 mcg/kg has been assessed on the basis of clinical experience in approved indications.

The efficacy of filgrastim was studied in a randomized, blinded, placebo-controlled study in a non-human primate model of radiation injury. The planned sample size was 62 animals, but the study was stopped at the interim analysis with 46 animals because efficacy was established. Rhesus macaques were randomized to a control (n = 22) or treated (n = 24) group. Animals were exposed to total body irradiation of 7.4 ± 0.15 Gy delivered at 0.8 ± 0.03 Gy/min, representing a dose that would be lethal in 50% of animals by 60 days of follow-up (LD50/60). Starting on day 1 after irradiation, animals received daily subcutaneous injections of placebo (5% dextrose in water) or filgrastim (10 mcg/kg/day). Blinded treatment was stopped when one of the following criteria was met: ANC ≥ 1,000/mm^3 for 3 consecutive days, or ANC ≥ 10,000/mm^3 for more than 2 consecutive days within study day 1 to 5, or ANC ≥ 10,000/mm^3 any time after study day 5. Animals received medical management consisting of intravenous fluids, antibiotics, blood transfusions, and other support as required.

Filgrastim significantly (at 0.023 level of significance) reduced 60-day mortality in the irradiated non-human primates: 21% mortality (5/24) in the filgrastim group compared to 59% mortality (13/22) in the control group.

16 HOW SUPPLIED/STORAGE AND HANDLING

ZARXIO injection is a clear, colorless to slightly yellowish, preservative-free solution supplied as:

Vial:

The vial is supplied in a carton containing one single-dose vial providing:

- 300 mcg/mL of filgrastim-sndz solution (NDC 61314-246-71)
- 480 mcg/1.6 (300 mcg/mL) mL of filgrastim-sndz solution (NDC 61314-266-73)

Latex sensitive individuals: The vial stopper is not made with natural rubber latex.

Prefilled syringe (BD UltraSafe Passive® Needle Guard):

Single-dose prefilled syringe containing 300 mcg/0.5 mL of filgrastim-sndz solution.

- Pack of 1 prefilled syringe (NDC 61314-318-01)
- Pack of 10 (multipack) prefilled syringes (NDC 61314-318-10)

Single-dose prefilled syringe containing 480 mcg/0.8 mL of filgrastim-sndz solution.

- Pack of 1 prefilled syringe (NDC 61314-326-01)
- Pack of 10 (multipack) prefilled syringes (NDC 61314-326-10)

Latex-sensitive individuals: The removable needle cap of ZARXIO prefilled syringe contains natural rubber latex which may cause allergic reaction. The safe use of ZARXIO in latex-sensitive individuals has not been studied.

Storage:

Store ZARXIO in the refrigerator at 2°C to 8°C (36°F to 46°F) in the original pack to protect from light. Do not leave ZARXIO in direct sunlight. Avoid shaking. Avoid freezing; if frozen, thaw in the refrigerator before administration. Discard ZARXIO if frozen more than once.

17 PATIENT COUNSELING INFORMATION

Advise the patient to read the FDA-approved patient labeling (Patient Information and Instructions for Use). Review the steps for direct patient administration with patients and caregivers. Training by the healthcare provider should aim to ensure that patients and caregivers can successfully perform all of the steps in the Instructions for Use of ZARXIO vial and prefilled syringe, including showing the patient or caregiver how to measure the required dose, particularly if a patient is on a dose other than the entire prefilled syringe. If a patient or caregiver is not able to demonstrate that they can measure the dose and administer the product successfully, you should consider whether the patient is an appropriate candidate for self-administration of ZARXIO or whether the patient would benefit from a different ZARXIO presentation.

Advise patients of the following risks and potential risks with ZARXIO:

- Rupture or enlargement of the spleen may occur. Symptoms include left upper quadrant abdominal pain or left shoulder pain. Advise patients to report pain in these areas to their physician immediately [see Warnings and Precautions (5.1)].
- Dyspnea, with or without fever, progressing to Acute Respiratory Distress Syndrome, may occur. Advise patients to report dyspnea to their physician immediately [see Warnings and Precautions (5.2)].
- Serious allergic reactions may occur, which may be signaled by rash‚ facial edema‚ wheezing‚ dyspnea‚ hypotension‚ or tachycardia. Advise patients to seek immediate medical attention if signs or symptoms of hypersensitivity reaction occur [see Warnings and Precautions (5.3)].
- In patients with sickle cell disease, sickle cell crisis and death have occurred. Discuss potential risks and benefits for patients with sickle cell disease prior to the administration of human granulocyte colony-stimulating factors [see Warnings and Precautions (5.4)].
- Glomerulonephritis may occur. Symptoms include swelling of the face or ankles, dark colored urine or blood in the urine, or a decrease in urine production. Advise patients to report signs or symptoms of glomerulonephritis to their physician immediately [see Warnings and Precautions (5.5)].
- There may be an increased risk of Myelodysplastic Syndrome and/or Acute Myeloid Leukemia in patients with congenital neutropenia who receive filgrastim products and in patients with breast and lung cancer who receive filgrastim products in conjunction with chemotherapy and/or radiation therapy. Symptoms of MDS and AML may include tiredness, fever, and easy bruising or bleeding. Advise patients to report to their physician signs and symptoms of MDS/AML [see Warnings and Precautions (5.8)].
- Cutaneous vasculitis may occur, which may be signaled by purpura or erythema. Advise patients to report signs or symptoms of vasculitis to their physician immediately [see Warnings and Precautions (5.11)].
- Aortitis may occur. Symptoms may include fever, abdominal pain, malaise, back pain, and increased inflammatory markers. Advise patients to report signs and symptoms of aortitis to their physician immediately [see Warnings and Precautions (5.15)].

Advise patients acutely exposed to myelosuppressive doses of radiation (Hematopoietic Syndrome of Acute Radiation Syndrome) that efficacy studies of filgrastim products for this indication could not be conducted in humans for ethical and feasibility reasons and that, therefore, approval of this use was based on efficacy studies conducted in animals [see Clinical Studies (14.6)].

Instruct patients who self-administer ZARXIO using the prefilled syringe or single-dose vial of the:

- Importance of following the applicable Instructions for Use.
- Dangers of reusing needles, syringes or unused portions of single-dose vials.
- Importance of following local requirements for proper disposal of used syringes, needles, and unused vials.
- Importance of informing the healthcare provider if difficulty occurs when measuring or administering partial contents of the ZARXIO prefilled syringe. If difficulties occur, use of the ZARXIO vial may be considered.
- Difference in product concentration of the ZARXIO prefilled syringe in comparison to the ZARXIO vial. When switching patients from the ZARXIO prefilled syringe to the ZARXIO vial, or vice versa, ensure that patients understand the correct volume to be administered since the concentration of ZARXIO differs between the prefilled syringe and the vial.

ZARXIO® (filgrastim-sndz)

UltraSafe and UltraSafe Passive are registered trademarks of Safety Syringes, Inc.

BD is a registered trademark of Becton, Dickinson and Company.

Manufactured by:

Sandoz Inc., Princeton, NJ 08540

US License No. 2003

Patient Information

ZARXIO® (zar-zee-oh)

(filgrastim-sndz)

injection

What is ZARXIO?

ZARXIO is a man-made form of granulocyte colony-stimulating factor (G‑CSF). G-CSF is a substance produced by the body. It stimulates the growth of neutrophils, a type of white blood cell important in the body’s fight against infection.

Acute Radiation Syndrome: The effectiveness of filgrastim for this use was only studied in animals, because it could not be studied in people.

Do not take ZARXIO if you have had a serious allergic reaction to human G-CSFs such as filgrastim products or pegfilgrastim products.

Before you take ZARXIO, tell your healthcare provider about all of your medical conditions, including if you:

- have a sickle cell disorder.
- have kidney problems.
- are receiving radiation therapy.
- are allergic to latex. The needle cap on the prefilled syringe contains dry natural rubber (derived from latex). You should not give ZARXIO using the prefilled syringe if you have latex allergies. Ask your healthcare provider about using the vial if you have latex allergies. The vial stopper is not made with natural rubber latex.
- are pregnant or plan to become pregnant. It is not known if ZARXIO will harm your unborn baby.
- are breastfeeding or plan to breastfeed. It is not known if ZARXIO passes into your breast milk.

Tell your healthcare provider about all the medicines you take, including prescription and over-the-counter medicines, vitamins, and herbal supplements.

How will I receive ZARXIO?

- ZARXIO injections can be given by a healthcare provider by intravenous (IV) infusion or under your skin (subcutaneous injection). Your healthcare provider may decide subcutaneous injections can be given at home by you or your caregiver. If ZARXIO is given at home, see the detailed “Instructions for Use” that comes with your ZARXIO for information on how to prepare and inject a dose of ZARXIO.
- You and your caregiver should be shown how to prepare and inject ZARXIO before you use it, by your healthcare provider.
- Your healthcare provider will tell you how much ZARXIO to inject and when to inject it. Do not change your dose or stop ZARXIO unless your healthcare provider tells you to.
- You should not inject a dose of ZARXIO less than 0.3 mL (180 mcg) from a ZARXIO prefilled syringe. A dose less than 0.3 mL cannot be accurately measured using the ZARXIO prefilled syringe.
- If you are receiving ZARXIO because you are also receiving chemotherapy, your dose of ZARXIO should be injected at least 24 hours before or 24 hours after your dose of chemotherapy. Your healthcare provider will do blood tests to monitor your white blood cell count, and if necessary, adjust your ZARXIO dose.
- If you are receiving ZARXIO because you have been suddenly (acutely) exposed to an amount of radiation that can affect your bone marrow (Acute Radiation Syndrome), you will need to have blood tests about every 3 days during treatment with ZARXIO to check your white blood cell count.
- If you miss a dose of ZARXIO, talk to your healthcare provider about when you should give your next dose.

What are the possible side effects of ZARXIO?

ZARXIO may cause serious side effects, including:

- Spleen rupture. Your spleen may become enlarged and can rupture. A ruptured spleen can cause death. Call your healthcare provider right away if you have pain in the left upper stomach (abdomen) area or your left shoulder.
- A serious lung problem called acute respiratory distress syndrome (ARDS). Call your healthcare provider or get emergency medical help right away if you have shortness of breath with or without a fever, trouble breathing, or a fast rate of breathing.
- Serious allergic reactions. ZARXIO can cause serious allergic reactions. These reactions can cause a rash over your whole body, shortness of breath, wheezing, dizziness, swelling around your mouth or eyes, fast heart rate, and sweating. If you have any of these symptoms, stop using ZARXIO and call your healthcare provider or get emergency medical help right away.
- Sickle cell crises. You may have a serious sickle cell crisis, which could lead to death, if you have a sickle cell disorder and receive ZARXIO. Call your healthcare provider right away if you have symptoms of sickle cell crisis such as pain or difficulty breathing.
- Kidney injury (glomerulonephritis). ZARXIO can cause kidney injury. Call your healthcare provider right away if you develop any of the following symptoms:
  - swelling of your face or ankles
  - blood in your urine or dark colored urine
  - you urinate less than usual
- Capillary leak syndrome. ZARXIO can cause fluid to leak from blood vessels into your body’s tissues. This condition is called “Capillary Leak Syndrome” (CLS). CLS can quickly cause you to have symptoms that may become life-threatening. Get emergency medical help right away if you develop any of the following symptoms:
  - swelling or puffiness and are urinating less than usual
  - trouble breathing
  - swelling of your stomach area (abdomen) and feeling of fullness
  - dizziness or feeling faint
  - a general feeling of tiredness
- Myelodysplastic syndrome (MDS) and acute myeloid leukemia (AML).
  - ZARXIO may increase the risk of developing a precancerous condition called MDS or a type of blood cancer called AML in people who were born with low white blood cell counts (congenital neutropenia).
  - If you have breast cancer or lung cancer, when ZARXIO is used with chemotherapy and radiation therapy, or with radiation therapy only, you may have an increased risk of developing MDS or AML.
  - Symptoms of MDS and AML may include tiredness, fever, and easy bruising or bleeding.
  - Call your healthcare provider if you develop any of these symptoms during treatment with ZARXIO.
- Decreased platelet count (thrombocytopenia). Your healthcare provider will check your blood during treatment with ZARXIO. Tell your healthcare provider if you have unusual bleeding or bruising during treatment with ZARXIO. This could be a sign of decreased platelet counts, which may reduce the ability of your blood to clot.
- Increased white blood cell count (leukocytosis). Your healthcare provider will check your blood during treatment with ZARXIO.
- Inflammation of your blood vessels (cutaneous vasculitis). Tell your healthcare provider right away if you develop purple spots or redness of your skin.
- Inflammation of the aorta (aortitis). Inflammation of the aorta (the large blood vessel which transports blood from the heart to the body) has been reported in patients who received filgrastim products. Symptoms may include fever, abdominal pain, feeling tired, and back pain. Call your healthcare provider if you experience these symptoms.

The most common side effects experienced in patients receiving ZARXIO include:

- Patients with cancer receiving chemotherapy: fever, pain, rash, cough, and shortness of breath
- Patients with acute myeloid leukemia receiving chemotherapy: pain, nose bleed, and rash
- Patients with cancer receiving chemotherapy followed by bone marrow transplant: rash
- Patients who are having their own blood cells collected: bone pain, fever, and headache
- Patients with severe chronic neutropenia: pain, decreased red blood cells, nose bleed, diarrhea, reduced sensation, and hair loss

These are not all the possible side effects of ZARXIO.

Call your healthcare provider for medical advice about side effects. You may report side effects to FDA at 1-800-FDA-1088.

How should I store ZARXIO?

- Store ZARXIO in the refrigerator between 36°F to 46°F (2°C to 8°C).
- Do not freeze.
- Store ZARXIO in the original pack to protect it from light or physical damage. Do not leave ZARXIO in direct sunlight.
- Do not shake ZARXIO.
- Take ZARXIO out of the refrigerator 30 minutes before use and allow it to reach room temperature between 68°F to 77°F (20°C to 25°C) before preparing an injection.
- If not used right away, ZARXIO may be kept at room temperature for up to 8 days. Throw away any ZARXIO that has been left at room temperature for longer than 8 days.
- After you inject your dose, throw away (dispose of) any unused ZARXIO left in the prefilled syringe or vial. Do not save unused ZARXIO in the prefilled syringe or vial for later use.

Keep ZARXIO and all medicines out of the reach of children.

General information about the safe and effective use of ZARXIO:

Medicines are sometimes prescribed for purposes other than those listed in a Patient Information leaflet. Do not use ZARXIO for a condition for which it was not prescribed. Do not give ZARXIO to other people, even if they have the same symptoms that you have. It may harm them. You can ask your pharmacist or healthcare provider for information about ZARXIO that is written for healthcare professionals.

What are the ingredients in ZARXIO?

Active ingredient: filgrastim-sndz

Inactive ingredients: glutamic acid, polysorbate 80, sodium hydroxide, sorbitol, water for injection

Manufactured by: Sandoz Inc., Princeton, NJ 08540, US License No. 2003

For more information visit www.zarxio.com or call 1-800-525-8747.

This Patient Information has been approved by the U.S. Food and Drug Administration. Revised: 10/2024

Instructions for Use

ZARXIO® (zar-zee-oh)

(filgrastim-sndz)

injection

Single-Dose Prefilled Syringe

Important Information You Need to Know Before Injecting ZARXIO:

- Do not inject yourself or someone else until you have been shown how to inject ZARXIO. Your healthcare provider will show you how to prepare and inject ZARXIO properly using the ZARXIO prefilled syringe with UltraSafe Passive® Needle Guard. Talk to your healthcare provider if you have any questions.
- You should not inject a dose of ZARXIO less than 0.3 mL (180 mcg) from a ZARXIO prefilled syringe. A dose less than 0.3 mL cannot be accurately measured using the ZARXIO prefilled syringe.
- Do not use the ZARXIO prefilled syringe if either the seal on the outer pack or the seal of the blister are broken.
- Keep the ZARXIO prefilled syringe in the sealed pack until you are ready to use it.
- The needle cap on the prefilled syringe contains natural rubber (derived from latex). Do not handle the prefilled syringe if you are allergic to latex.
- The prefilled syringe has a needle guard that will be activated to cover the needle after the injection is given. The needle guard will help prevent needle stick injuries to anyone who handles the prefilled syringe.
- Avoid touching the syringe needle guard wings before use. Touching them may cause the syringe needle guard to be activated too early.
- Do not remove the needle cap until just before you give the injection.
- Throw away (dispose of) the used ZARXIO prefilled syringe right away after use. Do not re-use a ZARXIO prefilled syringe. See “Disposing of used ZARXIO prefilled syringes” at the end of this Instructions for Use.
- Do not use if the syringe has been dropped onto a hard surface or dropped after removing the needle cap.

Storing ZARXIO

- Store ZARXIO in the refrigerator between 36°F to 46°F (2°C to 8°C).
- Protect from freezing ZARXIO. If frozen, thaw in the refrigerator before use. Throw away (dispose of) if it has been frozen more than 1 time.
- Store ZARXIO in the original pack to protect it from light.
- Avoid shaking ZARXIO.
- Take ZARXIO out of the refrigerator 30 minutes before use and allow it to reach room temperature between 68°F to 77°F (20°C to 25°C) before preparing an injection.
- If not used right away, ZARXIO may be kept at room temperature for up to 8 days. Throw away (dispose of) any ZARXIO that has been left at room temperature for longer than 8 days.
- After you inject your dose, throw away (dispose of) any unused ZARXIO left in the prefilled syringe. Do not save unused ZARXIO in the prefilled syringe for later use.

Keep ZARXIO and all medicines out of the reach of children.

About the ZARXIO prefilled syringe:

- ZARXIO prefilled syringes come in two strengths. Depending on your prescription, you will receive ZARXIO prefilled syringes that contain 300 mcg/0.5 mL or 480 mcg/0.8 mL of medicine. Your healthcare provider will determine the microgram (mcg) dose in milliliters (mL) that you will need to give based on your body weight. When you receive your ZARXIO prefilled syringes, always check to see that the:
  - name ZARXIO appears on the pack and prefilled syringe label.
  - expiration date on the prefilled syringe label has not passed. You should not use a prefilled syringe after the date on the label.
  - strength of ZARXIO (number of mcg on the pack containing the prefilled syringe) is the same as what your healthcare provider prescribed.

ZARXIO prefilled syringe parts (see Figure A). ZARXIO 300 mcg /0.5 mL prefilled syringe is shown as an example.

Figure A

What you need for your injection:

Included in the pack:

- A new ZARXIO prefilled syringe

Not included in the pack (see Figure B):

- 1 Alcohol wipe
- 1 Cotton ball or gauze
- Sharps disposal container
- 1 Adhesive bandage

Figure B

See “Disposing of used ZARXIO prefilled syringes” at the end of this Instructions for Use.

Preparing the ZARXIO prefilled syringe

Step 1. Find a clean, well-lit, flat work surface.

Step 2. Take the pack containing the ZARXIO prefilled syringe out of the refrigerator and leave it unopened on your work surface for about 30 minutes so that it reaches room temperature.

Step 3. Wash your hands well with soap and water.

Step 4. Remove the ZARXIO prefilled syringe from the outer pack and take it out of the blister.

Step 5. Check the expiration date. Do not use the ZARXIO prefilled syringe if the expiration date has passed.

Step 6. Look through the viewing window on the ZARXIO prefilled syringe. The liquid inside should be clear. The color may be colorless to slightly yellow. You may see a small air bubble in the liquid. This is normal. Do not use the prefilled syringe if the liquid contains visible particles, or if the liquid is cloudy or discolored. Return the ZARXIO prefilled syringe and the package it came in to your pharmacy.

Step 7. Do not use a ZARXIO prefilled syringe if it is broken. Return the broken prefilled syringe and the package it came in to your pharmacy.

Step 8. Check to make sure that the plastic transparent needle guard is covering the barrel of the glass syringe. If the transparent needle guard is covering the needle cap (see Figure C) the needle guard has already been activated. Do not use the prefilled syringe.

Get another prefilled syringe that has not been activated and is ready to use (see Figure D).

Figure C shows a needle guard that has already been activated. Do not use a ZARXIO prefilled syringe that has been activated.

Figure C Do Not Use

Figure D shows a needle guard that has not yet been activated. The prefilled syringe is ready for use.

Figure D Ready to Use

Step 9: Choose the injection site:

- Areas of your body that you may use as injection sites include:
  - the front of your thighs (see Figure E)
  - the lower stomach-area (abdomen), but not the area 2 inches around your navel (belly button) (see Figure E)
  - if a caregiver is giving you the injection
  - upper outer arms (see Figure E and Figure F)
  - upper areas of the buttocks (see Figure F)
- Choose a different site each time you give yourself an injection.
- Do not inject into areas where the skin is tender, bruised, red, scaly, or hard. Avoid areas with scars or stretch marks.

Figure E

Figure F

Step 10. Clean the injection site using a circular motion with the alcohol wipe. Leave it to dry before injecting. Do not touch the cleaned area again before injecting.

Giving your injection

Step 11. Hold the prefilled syringe by the body (the clear plastic needle guard) with the needle pointing up (see Figure G). Holding the syringe with the needle pointing up helps to prevent medicine from leaking out of the needle. Carefully pull the needle cap straight off. Throw away the needle cap.

Figure G

Step 12. Check the syringe for an air bubble. Gently tap the syringe body with your fingers until the air bubble rises to the top of the syringe (see Figure H). Slowly push the plunger up to push any air out of the syringe and stop when you see a small drop start to appear at the needle tip (see Figure H).

Figure H

- Your healthcare provider has prescribed either a “full” syringe dose or a “partial” syringe dose of ZARXIO. If you are prescribed a full dose, you will inject all of the medicine from your prefilled syringe. For a full dose, go directly to Step 14.
- If you are prescribed a partial dose of ZARXIO, start with Step 13.
Step 13. Holding the syringe as shown, press slowly on the plunger to push out the excess medicine until the edge of the conical base of the plunger stopper lines up with the syringe marking for your prescribed dose. See Figure I, example for a dose of 0.4 mL. Your dose may be different than the example shown.

Be careful not to touch the needle guard wings before use. The needle guard may be activated too early.

Check again to make sure the correct dose of ZARXIO is in the syringe.

Call your healthcare provider if you have problems measuring or injecting your dose of ZARXIO.

Figure I

Step 14. With one hand gently pinch the skin at the injection site. With your other hand insert the needle into your skin as shown (see Figure J). Push the needle all the way in to make sure that you inject your full dose.

Figure J

Step 15. Hold the ZARXIO prefilled syringe as shown (see Figure K). Slowly press down on the plunger as far as it will go so that the plunger head is completely between the needle guard wings.

Figure K

Step 16. Keep the plunger fully pressed down while you carefully pull the needle straight out from the injection site (see Figure L).

Figure L

Step 17. Slowly release the plunger and allow the needle guard to automatically cover the exposed needle (see Figure M).

Figure M

Step 18. There may be a small amount of blood at the injections site. You can press a cotton ball or gauze over the injection site and hold it for 10 seconds. Do not rub the injection site. You may cover the injection site with a small adhesive bandage, if needed.

Disposing of used ZARXIO prefilled syringes

Put your used prefilled syringes in an FDA-cleared sharps disposal container right away after use (see Figure N). Do not throw away (dispose of) ZARXIO prefilled syringes in your household trash.

Figure N

If you do not have an FDA-cleared sharps disposal container, you may use a household container that is:

- made of a heavy-duty plastic,
- can be closed with a tight-fitting, puncture-resistant lid, without sharps being able to come out,
- upright and stable during use,
- leak-resistant, and
- properly labeled to warn of hazardous waste inside the container.

When your sharps disposal container is almost full, you will need to follow your community guidelines for the right way to dispose of your sharps disposal container. There may be state or local laws about how you should throw away used needles, syringes, and prefilled syringes. For more information about safe sharps disposal, and for specific information about sharps disposal in the state that you live in, go to the FDA’s website at: http://www.fda.gov/safesharpsdisposal.

Do not reuse the prefilled syringe.

Do not recycle the syringe, or sharps disposal container or throw them into household trash.

Important: Always keep the sharps disposal container out of the reach of children.

This Instructions for Use has been approved by the U.S. Food and Drug Administration.

Manufactured by:

Sandoz Inc., Princeton, NJ 08540,

US License No. 2003

Revised: 08/2024

Instructions for Use

ZARXIO® (zar-zee-oh)

(filgrastim-sndz)

Injection

Single-Dose Vial

Important Information You Need to Know Before Injecting ZARXIO:

- Do not inject yourself or someone else until you have been shown how to inject ZARXIO. Your healthcare provider will show you how to prepare and inject ZARXIO properly using the ZARXIO vial and syringe. Talk to your healthcare provider if you have any questions.
- Do not use the ZARXIO vial if either the seal on the outer pack or the cap of the vial is broken.
- Keep the ZARXIO vial in the sealed pack until you are ready to use it.
- Throw away (dispose of) the used ZARXIO vials, syringes, and needles right away after use. Do not re-use ZARXIO vials, syringes, or needles. See “Disposing of used ZARXIO vials, syringes, and needles” at the end of this Instructions for Use.
- Latex-sensitive individuals: The vial stopper is not made with natural rubber latex.

Storing ZARXIO

- Store ZARXIO in the refrigerator between 36°F to 46°F (2°C to 8°C).
- Protect ZARXIO from freezing. If frozen, thaw in the refrigerator before use. Throw away (dispose of) if it has been frozen more than 1 time.
- Store ZARXIO in the original pack to protect it from light.
- Avoid shaking ZARXIO.
- Take ZARXIO out of the refrigerator 30 minutes before use and allow it to reach room temperature between 68°F to 77°F (20°C to 25°C) before preparing an injection.
- If not used right away, ZARXIO may be kept at room temperature for up to 8 days. Throw away (dispose of) any ZARXIO that has been left at room temperature for longer than 8 days.
- After you inject your dose, throw away (dispose of) any unused ZARXIO left in the vial. Do not save unused ZARXIO in the vial for later use.

Keep ZARXIO and all medicines out of the reach of children.

About the ZARXIO vial:

- ZARXIO vials come in two strengths. Depending on your prescription, you will receive ZARXIO vials that contain 300 mcg/mL or 480 mcg/1.6 mL of medicine. Your healthcare provider will determine the microgram (mcg) dose in milliliters (mL) that you will need to give based on your body weight.
- When you receive your ZARXIO vials, always check to see that:
  - the name ZARXIO appears on the pack and vial label.
  - the expiration date on the vial label has not passed. You should not use a vial after the date on the label.
  - the strength of ZARXIO (number of mcg on the pack containing the vial) is the same as what your healthcare provider prescribed.

What you need for your injection:

Included in the pack (see Figure A):

- A new ZARXIO vial

Figure A

Not included in the pack (see Figure B):

- New disposable syringe and needle
- 2 Alcohol wipes
- Cotton ball or gauze
- Sharps disposal container
- Adhesive bandage

Figure B

- Only use the disposable syringes and needles that your healthcare provider prescribes.
- Only use the syringes and needles 1 time. Discard (throw away) any used syringes and needles.
- You should only use a syringe that is marked in tenths of milliliters (mL).
- Your healthcare provider will show you how to measure the correct dose of ZARXIO. This dose will be measured in milliliters (mL).

See “Disposing of used ZARXIO vials, syringes, and needles” at the end of this Instructions for Use.

Preparing the ZARXIO injection

Step 1. Find a clean, well-lit, flat work surface.

Step 2. Take the ZARXIO vial out of the refrigerator and leave it unopened on your work surface for about 30 minutes so that it reaches room temperature.
Step 3. Wash your hands well with soap and water.
Step 4. Remove the ZARXIO vial from the outer pack.
Step 5. Check the expiration date. Do not use the ZARXIO vial if the expiration date has passed.
Step 6. Inspect the ZARXIO vial. The liquid inside should be clear. The color may be colorless to slightly yellow. Do not use the vial if the liquid contains visible particles, or if the liquid is cloudy or discolored. Return the ZARXIO vial and the package it came into your pharmacy.
Step 7. Do not use a ZARXIO vial if the cap is damaged. Return the vial with damaged cap and the package it came into your pharmacy.
Step 8. Take the cap off the vial. Clean the rubber stopper with one alcohol wipe (see Figure C).

Figure C

Step 9. Check the carton containing the syringe. If the carton has been opened or damaged, do not use that syringe. Dispose of (throw away) that syringe in the sharps disposal container.
Step 10. Hold the syringe by the barrel with the needle cap pointing up (see Figure D). Carefully pull the needle cap straight off and away from your body. Throw away the needle cap into the sharps disposal container.

Figure D

Step 11. Pull back on the plunger and draw air into the syringe that is the same amount (mL) as the dose of ZARXIO that your healthcare provider prescribed.
Step 12. Keep the vial on the flat working surface and insert the needle straight down through the rubber stopper. Do not insert the needle through the rubber stopper more than 1 time.
Step 13. Push the plunger down and inject all the air from the syringe into the vial of ZARXIO (see Figure E).

Figure E

Step 14. Keep the needle in the vial and turn the vial upside down (see Figure F). Make sure that the ZARXIO liquid is covering the tip of the needle.

Figure F

Step 15. Keep the vial upside down and slowly pull back on the plunger to fill the syringe barrel with ZARXIO to the correct marking amount (mL) of medicine that matches the dose your healthcare provider prescribed.
Step 16. Keep the needle in the vial and check for air bubbles in the syringe. If there are air bubbles, gently tap the syringe barrel with your finger until the air bubbles rise to the top (see Figure G). Slowly push the plunger up to push the air bubbles out of the syringe.

Figure G

Step 17. Keep the tip of the needle in the liquid and again pull the plunger back to the number on the syringe barrel that matches your dose. Check again for air bubbles. The air in the syringe will not hurt you, but too large an air bubble can reduce your dose of ZARXIO. If there are still air bubbles, repeat the steps above to remove them.

Step 18. Check again to make sure that you have the correct dose in the syringe. It is important that you use the exact dose prescribed by your healthcare provider. Do not remove the needle from the vial. Lay the vial down on its side with the needle still in the vial.

Step 19: Choose the injection site:

- Areas of your body that you may use as injection sites include:
  - the front of your thighs (see Figure H)
  - the lower stomach-area (abdomen), but not the area 2 inches around your navel (belly button) (see Figure H)
  - if a caregiver is giving you the injection
    - upper outer arms (see Figure H and Figure I)
    - upper areas of the buttocks (see Figure I)
- Choose a different site each time you give yourself an injection.
- Do not inject into areas where the skin is tender, bruised, red, scaly, or hard. Avoid areas with scars or stretch marks.

Figure H

Figure I

Step 20. Clean the injection site using a circular motion with the alcohol wipe. Leave it to dry before injecting. Do not touch the cleaned area again before injecting.

Giving your injection

Step 21. Remove the prepared syringe and needle from the vial.
Step 22. With one hand gently pinch the skin at the injection site. With your other hand insert the needle into your skin at a 45 to 90 degree angle as shown (see Figure J). Push the needle all the way in to make sure that you inject your full dose.

Figure J

Step 23. Hold the syringe as shown (see Figure K). Slowly press down on the plunger as far as it will go.

Figure K

Step 24. Keep the plunger fully pressed down while you carefully pull the needle straight out from the injection site.

Step 25. There may be a small amount of blood at the injection site. You can press a cotton ball or gauze over the injection site and hold it for 10 seconds. Do not rub the injection site. You may cover the injection site with a small adhesive bandage, if needed.

Disposing of used ZARXIO vials, syringes, and needles

Put your used vials, syringes, and needles in an FDA-cleared sharps disposal container right away after use (see Figure L). Do not throw away (dispose of) vials, syringes, and needles in your household trash.

Figure L

If you do not have an FDA-cleared sharps disposal container, you may use a household container that is:

- made of a heavy-duty plastic,
- can be closed with a tight-fitting, puncture-resistant lid, without sharps being able to come out,
- upright and stable during use,
- leak-resistant, and
- properly labeled to warn of hazardous waste inside the container.

When your sharps disposal container is almost full, you will need to follow your community guidelines for the right way to dispose of your sharps disposal container. There may be state or local laws about how you should throw away used syringes and vials. For more information about safe sharps disposal, and for specific information about sharps disposal in the state that you live in, go to the FDA’s website at: http://www.fda.gov/safesharpsdisposal.

Do not reuse the vial or syringe.

Do not recycle the vial, syringe, or sharps disposal container or throw them into household trash.

Important: Always keep the sharps disposal container out of the reach of children.

This Instructions for Use has been approved by the U.S. Food and Drug Administration.

Manufactured by: Sandoz Inc., Princeton, NJ 08540, US License No. 2003

Approved: 08/2024

300 mcg PFS Carton

Zarxio®

(filgrastim-sndz)

Injection

For Subcutaneous Use or

Intravenous Use Only

Single-Dose Only

1 prefilled syringe with a needle guard

300 mcg/0.5 mL

NDC 61314-318-01

A recombinant Granulocyte Colony-Stimulating Factor (rG-CSF)

derived from E Coli.

No Preservative.

Refrigerate. Protect from freezing.

Caution: Contains Natural Rubber Latex

Which May Cause Allergic Reaction.

Rx only

SANDOZ

480 mcg PFS Carton

Zarxio®

(filgrastim-sndz)

Injection

For Subcutaneous Use or

Intravenous Use Only

Single-Dose Only

1 prefilled syringe with a needle guard

480 mcg/0.8 mL

NDC 61314-326-01

A recombinant Granulocyte Colony-Stimulating Factor (rG-CSF)

derived from E Coli.

No Preservative.

Refrigerate. Protect from freezing.

Caution: Contains Natural Rubber Latex

Which May Cause Allergic Reaction.

Rx only

SANDOZ